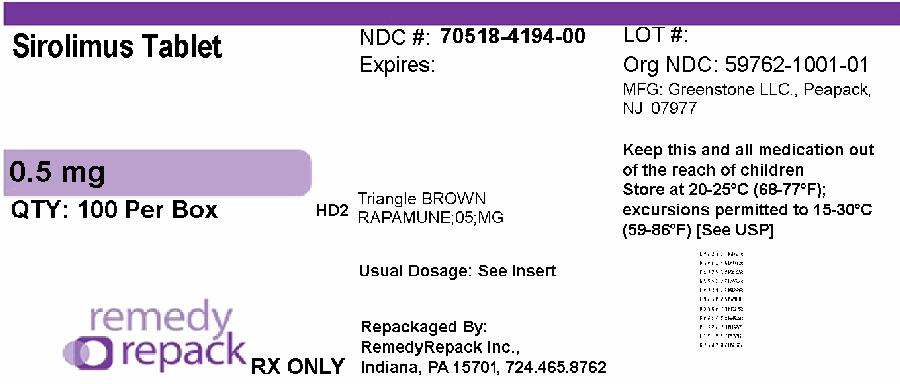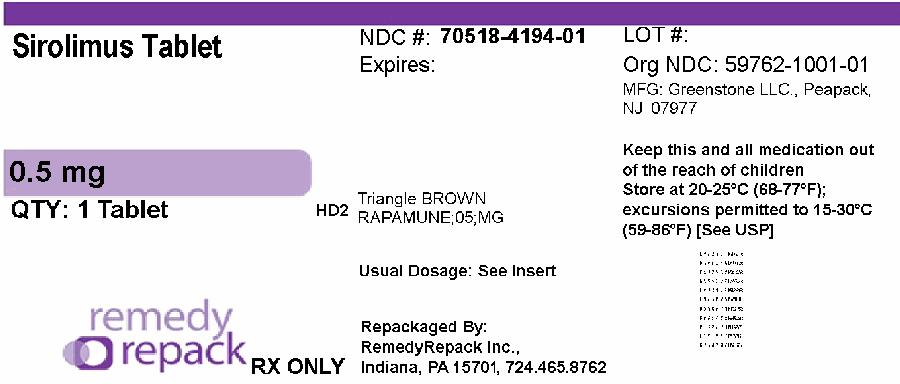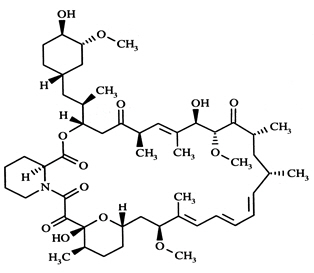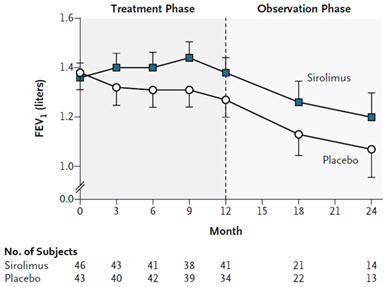 DRUG LABEL: Sirolimus
NDC: 70518-4194 | Form: TABLET, SUGAR COATED
Manufacturer: REMEDYREPACK INC.
Category: prescription | Type: HUMAN PRESCRIPTION DRUG LABEL
Date: 20250929

ACTIVE INGREDIENTS: SIROLIMUS 0.5 mg/1 1
INACTIVE INGREDIENTS: SUCROSE; POLYETHYLENE GLYCOL 8000; CALCIUM SULFATE, UNSPECIFIED FORM; MICROCRYSTALLINE CELLULOSE; TALC; TITANIUM DIOXIDE; MAGNESIUM STEARATE; POVIDONE K30; LACTOSE MONOHYDRATE; POLOXAMER 188; CARNAUBA WAX; FERRIC OXIDE YELLOW; .ALPHA.-TOCOPHEROL ACETATE; GLYCERYL OLEATE

HIGHLIGHTS OF PRESCRIBING INFORMATION

These highlights do not include all the information needed to use SIROLIMUS safely and effectively. See full prescribing information for SIROLIMUS.
SIROLIMUS tablets, for oral use
Initial U.S. Approval: 1999

WARNING: IMMUNOSUPPRESSION, USE IS NOT RECOMMENDED IN LIVER OR LUNG TRANSPLANT PATIENTS

See full prescribing information for complete boxed warning.

- Increased susceptibility to infection and the possible development of lymphoma and other malignancies may result from immunosuppression (5.1). Only physicians experienced in immunosuppressive therapy and management of renal transplant patients should use sirolimus for prophylaxis of organ rejection in patients receiving renal transplants.
- The safety and efficacy of sirolimus as immunosuppressive therapy have not been established in liver or lung transplant patients, and therefore, such use is not recommended (5.2, 5.3).
  - Liver Transplantation – Excess mortality, graft loss, and hepatic artery thrombosis (5.2).
  - Lung Transplantation – Bronchial anastomotic dehiscence (5.3).

1 INDICATIONS AND USAGE

Sirolimus is an mTOR inhibitor immunosuppressant indicated for the prophylaxis of organ rejection in patients aged ≥13 years receiving renal transplants:

- Patients at low- to moderate-immunologic risk: Use initially with cyclosporine (CsA) and corticosteroids. CsA withdrawal is recommended 2–4 months after transplantation (1.1).
- Patients at high-immunologic risk: Use in combination with CsA and corticosteroids for the first 12 months following transplantation (1.1). Safety and efficacy of CsA withdrawal has not been established in high risk patients (1.1, 1.2, 14.3).

Sirolimus is an mTOR inhibitor indicated for the treatment of patients with lymphangioleiomyomatosis (1.3).

2 DOSAGE AND ADMINISTRATION

Renal Transplant Patients:

- Administer once daily by mouth, consistently with or without food (2).
- Administer the initial dose as soon as possible after transplantation and 4 hours after CsA (2.1, 7.1).
- Adjust the sirolimus maintenance dose to achieve sirolimus trough concentrations within the target-range (2.5).
- Hepatic impairment: Reduce maintenance dose in patients with hepatic impairment (2.7, 8.6, 12.3).

In renal transplant patients at low- to moderate-immunologic risk:

- Sirolimus and CsA Combination Therapy: One loading dose of 6 mg on day 1, followed by daily maintenance doses of 2 mg (2.2).
- Sirolimus Following CsA Withdrawal: 2–4 months post-transplantation, withdraw CsA over 4–8 weeks (2.2).

In renal transplant patients at high-immunologic risk:

- Sirolimus and CsA Combination Therapy (for the first 12 months post-transplantation): One loading dose of up to 15 mg on day 1, followed by daily maintenance doses of 5 mg (2.3).

Lymphangioleiomyomatosis Patients:

- Administer once daily by mouth, consistently with or without food (2).
- Recommended initial sirolimus dose is 2 mg/day (2.4).
- Adjust the sirolimus dose to achieve sirolimus trough concentrations between 5–15 ng/mL (2.4).
- Hepatic impairment: Reduce maintenance dose in patients with hepatic impairment (2.7, 8.6, 12.3).

Therapeutic drug monitoring is recommended for all patients (2.5, 5.17).

3 DOSAGE FORMS AND STRENGTHS

- Tablets: 0.5 mg, 1 mg, 2 mg (3.1).

4 CONTRAINDICATIONS

Hypersensitivity to sirolimus (4).

5 WARNINGS AND PRECAUTIONS

- Hypersensitivity Reactions (5.4)
- Angioedema (5.5)
- Fluid Accumulation and Impairment of Wound Healing (5.6)
- Hyperlipidemia (5.7)
- Decline in Renal Function (5.8)
- Proteinuria (5.9)
- Latent Viral Infections (5.10)
- Interstitial Lung Disease/Non-Infectious Pneumonitis (5.11)
- De NovoUse Without Cyclosporine (5.12)
- Increased Risk of Calcineurin Inhibitor-Induced Hemolytic Uremic Syndrome/ Thrombotic Thrombocytopenic Purpura/ Thrombotic Microangiopathy (5.13)
- Embryo-Fetal Toxicity: Can cause fetal harm. Use of highly effective contraception is recommended for females of reproductive potential during treatment and for 12 weeks after final dose of sirolimus (5.15, 8.1)
- Male Infertility: Azoospermia or oligospermia may occur (5.16, 13.1)
- Immunizations: Avoid live vaccines (5.19)

6 ADVERSE REACTIONS

Prophylaxis of organ rejection in patients receiving renal transplants: Most common adverse reactions (incidence ≥30%) are peripheral edema, hypertriglyceridemia, hypertension, hypercholesterolemia, creatinine increased, abdominal pain, diarrhea, headache, fever, urinary tract infection, anemia, nausea, arthralgia, pain, and thrombocytopenia (6).
Lymphangioleiomyomatosis: Most common adverse reactions (incidence ≥20%) are stomatitis, diarrhea, abdominal pain, nausea, nasopharyngitis, acne, chest pain, peripheral edema, upper respiratory tract infection, headache, dizziness, myalgia, and hypercholesterolemia (6.6).
To report SUSPECTED ADVERSE REACTIONS, contact Greenstone LLC Professional Information Services at 1-877-446-3679 or FDA at 1-800-FDA-1088 or www.fda.gov/medwatch

7 DRUG INTERACTIONS

- Avoid concomitant use with strong CYP3A4/P-gp inducers or strong CYP3A4/P-gp inhibitors that decrease or increase sirolimus concentrations (7.4, 12.3).
- Therapeutic drug monitoring and dose reduction for sirolimus should be considered when sirolimus is co-administered with cannabidiol (5.21, 7.5).
- See full prescribing information for complete list of clinically significant drug interactions (12.3).

8 USE IN SPECIFIC POPULATIONS

- Pregnancy: Based on animal data can cause fetal harm (5.15, 8.1).
- Lactation: Potential for serious adverse effects in breastfed infants based on mechanism of action (8.2).
- Females and Males of Reproductive Potential: May impair fertility (8.1, 8.3, 13.1).

FULL PRESCRIBING INFORMATION

WARNING: IMMUNOSUPPRESSION, USE IS NOT RECOMMENDED IN LIVER OR LUNG TRANSPLANT PATIENTS

- Increased susceptibility to infection and the possible development of lymphoma and other malignancies may result from immunosuppression

Increased susceptibility to infection and the possible development of lymphoma may result from immunosuppression. Only physicians experienced in immunosuppressive therapy and management of renal transplant patients should use sirolimus for prophylaxis of organ rejection in patients receiving renal transplants. Patients receiving the drug should be managed in facilities equipped and staffed with adequate laboratory and supportive medical resources. The physician responsible for maintenance therapy should have complete information requisite for the follow-up of the patient [ see Warnings and Precautions (5.1)] .

- The safety and efficacy of sirolimus as immunosuppressive therapy have not been established in liver or lung transplant patients, and therefore, such use is not recommended [ see Warnings and Precautions (5.2, 5.3)] .
- Liver Transplantation – Excess Mortality, Graft Loss, and Hepatic Artery Thrombosis (HAT)

The use of sirolimus in combination with tacrolimus was associated with excess mortality and graft loss in a study in de novoliver transplant patients. Many of these patients had evidence of infection at or near the time of death.

In this and another study in de novoliver transplant patients, the use of sirolimus in combination with cyclosporine or tacrolimus was associated with an increase in HAT; most cases of HAT occurred within 30 days post-transplantation and most led to graft loss or death [ see Warnings and Precautions (5.2)].

- Lung Transplantation – Bronchial Anastomotic Dehiscence

Cases of bronchial anastomotic dehiscence, most fatal, have been reported in de novo lung transplant patients when sirolimus has been used as part of an immunosuppressive regimen [ see Warnings and Precautions (5.3)].

1 INDICATIONS AND USAGE

1.1 Prophylaxis of Organ Rejection in Renal Transplantation

Sirolimus is indicated for the prophylaxis of organ rejection in patients aged 13 years or older receiving renal transplants.

In patients at low- to moderate-immunologic risk,it is recommended that sirolimus be used initially in a regimen with cyclosporine and corticosteroids; cyclosporine should be withdrawn 2 to 4 months after transplantation [ see Dosage and Administration (2.2)].

In patients at high-immunologic risk(defined as Black recipients and/or repeat renal transplant recipients who lost a previous allograft for immunologic reason and/or patients with high panel-reactive antibodies [PRA; peak PRA level >80%]), it is recommended that sirolimus be used in combination with cyclosporine and corticosteroids for the first year following transplantation [ see Dosage and Administration (2.3), Clinical Studies (14.3)].

1.2 Limitations of Use in Renal Transplantation

Cyclosporine withdrawal has not been studied in patients with Banff Grade 3 acute rejection or vascular rejection prior to cyclosporine withdrawal, those who are dialysis-dependent, those with serum creatinine >4.5 mg/dL, Black patients, patients of multi-organ transplants, secondary transplants, or those with high levels of panel-reactive antibodies [ see Clinical Studies (14.2)].

In patients at high-immunologic risk,the safety and efficacy of sirolimus used in combination with cyclosporine and corticosteroids has not been studied beyond one year; therefore after the first 12 months following transplantation, any adjustments to the immunosuppressive regimen should be considered on the basis of the clinical status of the patient [ see Clinical Studies (14.3)].

In pediatric patients,the safety and efficacy of sirolimus have not been established in patients <13 years old, or in pediatric (<18 years) renal transplant patients considered at high-immunologic risk [ see Adverse Reactions (6.5), Clinical Studies (14.6)].

The safety and efficacy of de novouse of sirolimus without cyclosporine have not been established in renal transplant patients [ see Warnings and Precautions (5.12)].

The safety and efficacy of conversion from calcineurin inhibitors to sirolimusin maintenance renal transplant patients have not been established [ see Clinical Studies (14.4)].

1.3 Treatment of Patients with Lymphangioleiomyomatosis

Sirolimus is indicated for the treatment of patients with lymphangioleiomyomatosis (LAM).

2 DOSAGE AND ADMINISTRATION

Sirolimus is to be administered orally once daily, consistently with or without food [ see Dosage and Administration (2.5), Clinical Pharmacology (12.3)].

Tablets should not be crushed, chewed or split. Patients unable to take the tablets should be prescribed the solution and instructed in its use.

2.1 General Dosing Guidance for Renal Transplant Patients

The initial dose of sirolimus should be administered as soon as possible after transplantation. It is recommended that sirolimus be taken 4 hours after administration of cyclosporine oral solution (MODIFIED) and or/cyclosporine capsules (MODIFIED) [ see Drug Interactions (7.2)].

Frequent sirolimus dose adjustments based on non-steady-state sirolimus concentrations can lead to overdosing or underdosing because sirolimus has a long half-life. Once sirolimus maintenance dose is adjusted, patients should continue on the new maintenance dose for at least 7 to 14 days before further dosage adjustment with concentration monitoring. In most patients, dose adjustments can be based on simple proportion: new sirolimus dose = current dose × (target concentration/current concentration). A loading dose should be considered in addition to a new maintenance dose when it is necessary to increase sirolimus trough concentrations: sirolimus loading dose = 3 × (new maintenance dose - current maintenance dose). The maximum sirolimus dose administered on any day should not exceed 40 mg. If an estimated daily dose exceeds 40 mg due to the addition of a loading dose, the loading dose should be administered over 2 days. Sirolimus trough concentrations should be monitored at least 3 to 4 days after a loading dose(s).

Two milligrams (2 mg) of sirolimus oral solution have been demonstrated to be clinically equivalent to 2 mg sirolimus tablets; hence, at this dose these two formulations are interchangeable. However, it is not known if higher doses of sirolimus oral solution are clinically equivalent to higher doses of sirolimus tablets on a mg-to-mg basis [ see Clinical Pharmacology (12.3)].

2.2 Renal Transplant Patients at Low- to Moderate-Immunologic Risk

Sirolimus and Cyclosporine Combination Therapy

For de novorenal transplant patients, it is recommended that sirolimus tablets be used initially in a regimen with cyclosporine and corticosteroids. A loading dose of sirolimus equivalent to 3 times the maintenance dose should be given, i.e. a daily maintenance dose of 2 mg should be preceded with a loading dose of 6 mg. Therapeutic drug monitoring should be used to maintain sirolimus drug concentrations within the target-range [ see Dosage and Administration (2.5)].

Sirolimus Following Cyclosporine Withdrawal

At 2 to 4 months following transplantation, cyclosporine should be progressively discontinued over 4 to 8 weeks, and the sirolimus dose should be adjusted to obtain sirolimus whole blood trough concentrations within the target-range [ see Dosage and Administration (2.5)]. Because cyclosporine inhibits the metabolism and transport of sirolimus, sirolimus concentrations may decrease when cyclosporine is discontinued, unless the sirolimus dose is increased [ see Clinical Pharmacology (12.3)].

2.3 Renal Transplant Patients at High-Immunologic Risk

In patients with high-immunologic risk, it is recommended that sirolimus be used in combination with cyclosporine and corticosteroids for the first 12 months following transplantation [ see Clinical Studies (14.3)]. The safety and efficacy of this combination in high-immunologic risk patients has not been studied beyond the first 12 months. Therefore, after the first 12 months following transplantation, any adjustments to the immunosuppressive regimen should be considered on the basis of the clinical status of the patient.

For patients receiving sirolimus with cyclosporine, sirolimus therapy should be initiated with a loading dose of up to 15 mg on day 1 post-transplantation. Beginning on day 2, an initial maintenance dose of 5 mg/day should be given. A trough level should be obtained between days 5 and 7, and the daily dose of sirolimus should thereafter be adjusted [ see Dosage and Administration (2.5)].

The starting dose of cyclosporine should be up to 7 mg/kg/day in divided doses and the dose should subsequently be adjusted to achieve target whole blood trough concentrations [ see Dosage and Administration (2.5)]. Prednisone should be administered at a minimum of 5 mg/day.

Antibody induction therapy may be used.

2.4 Dosing in Patients with Lymphangioleiomyomatosis

For patients with lymphangioleiomyomatosis, the initial Sirolimus dose should be 2 mg/day. Sirolimus whole blood trough concentrations should be measured in 10–20 days, with dosage adjustment to maintain concentrations between 5–15 ng/mL [ see Dosage and Administration (2.5)].

In most patients, dose adjustments can be based on simple proportion: new Sirolimus dose = current dose × (target concentration/current concentration). Frequent Sirolimus dose adjustments based on non-steady-state sirolimus concentrations can lead to overdosing or under dosing because sirolimus has a long half-life. Once Sirolimus maintenance dose is adjusted, patients should continue on the new maintenance dose for at least 7 to 14 days before further dosage adjustment with concentration monitoring. Once a stable dose is achieved, therapeutic drug monitoring should be performed at least every three months.

2.5 Therapeutic Drug Monitoring

Monitoring of sirolimus trough concentrations is recommended for all patients, especially in those patients likely to have altered drug metabolism, in patients ≥13 years who weigh less than 40 kg, in patients with hepatic impairment, when a change in the sirolimus dosage form is made, and during concurrent administration of strong CYP3A4 inducers and inhibitors [ see Warnings and Precautions (5.20, 5.21), Drug Interactions (7)].

Therapeutic drug monitoring should not be the sole basis for adjusting sirolimus therapy. Careful attention should be made to clinical signs/symptoms, tissue biopsy findings, and laboratory parameters.

When used in combination with cyclosporine, sirolimus trough concentrations should be maintained within the target-range [ see Clinical Studies (14), Clinical Pharmacology (12.3)]. Following cyclosporine withdrawal in transplant patients at low- to moderate-immunologic risk, the target sirolimus trough concentrations should be 16 to 24 ng/mL for the first year following transplantation. Thereafter, the target sirolimus concentrations should be 12 to 20 ng/mL.

The above recommended 24-hour trough concentration ranges for sirolimus are based on chromatographic methods. Currently in clinical practice, sirolimus whole blood concentrations are being measured by both chromatographic and immunoassay methodologies. Because the measured sirolimus whole blood concentrations depend on the type of assay used, the concentrations obtained by these different methodologies are not interchangeable [ see Warnings and Precautions (5.17), Clinical Pharmacology (12.3)]. Adjustments to the targeted range should be made according to the assay utilized to determine sirolimus trough concentrations. Since results are assay and laboratory dependent, and the results may change over time, adjustments to the targeted therapeutic range must be made with a detailed knowledge of the site-specific assay used. Therefore, communication should be maintained with the laboratory performing the assay. A discussion of different assay methods is contained in Clinical Therapeutics, Volume 22, Supplement B, April 2000 [ see References (15)].

2.6 Patients with Low Body Weight

The initial dosage in patients ≥13 years who weigh less than 40 kg should be adjusted, based on body surface area, to 1 mg/m^2/day. The loading dose should be 3 mg/m^2.

2.7 Patients with Hepatic Impairment

It is recommended that the maintenance dose of sirolimus be reduced by approximately one third in patients with mild or moderate hepatic impairment and by approximately one half in patients with severe hepatic impairment. It is not necessary to modify the sirolimus loading dose [ see Use in Specific Populations (8.6), Clinical Pharmacology (12.3)].

2.8 Patients with Renal Impairment

Dosage adjustment is not needed in patients with impaired renal function [ see Use in Specific Populations (8.7)].

3 DOSAGE FORMS AND STRENGTHS

3.1 Sirolimus Tablets

- 0.5 mg, tan, triangular-shaped tablets marked "RAPAMUNE 0.5 mg" on one side.

4 CONTRAINDICATIONS

Sirolimus is contraindicated in patients with a hypersensitivity to sirolimus [ see Warnings and Precautions (5.4)].

5 WARNINGS AND PRECAUTIONS

5.1 Increased Susceptibility to Infection and the Possible Development of Lymphoma

Increased susceptibility to infection and the possible development of lymphoma and other malignancies, particularly of the skin, may result from immunosuppression. The rates of lymphoma/lymphoproliferative disease observed in Studies 1 and 2 were 0.7–3.2% (for sirolimus -treated patients) versus 0.6–0.8% (azathioprine and placebo control) [ see Adverse Reactions (6.1)and (6.2)]. Oversuppression of the immune system can also increase susceptibility to infection, including opportunistic infections such as tuberculosis, fatal infections, and sepsis. Only physicians experienced in immunosuppressive therapy and management of organ transplant patients should use sirolimus for prophylaxis of organ rejection in patients receiving renal transplants. Patients receiving the drug should be managed in facilities equipped and staffed with adequate laboratory and supportive medical resources. The physician responsible for maintenance therapy should have complete information requisite for the follow-up of the patient.

5.2 Liver Transplantation – Excess Mortality, Graft Loss, and Hepatic Artery Thrombosis

The safety and efficacy of sirolimus as immunosuppressive therapy have not been established in liver transplant patients; therefore, such use is not recommended. The use of sirolimus has been associated with adverse outcomes in patients following liver transplantation, including excess mortality, graft loss and hepatic artery thrombosis (HAT).

In a study in de novoliver transplant patients, the use of sirolimus in combination with tacrolimus was associated with excess mortality and graft loss (22% in combination versus 9% on tacrolimus alone). Many of these patients had evidence of infection at or near the time of death.

In this and another study in de novoliver transplant patients, the use of sirolimus in combination with cyclosporine or tacrolimus was associated with an increase in HAT (7% in combination versus 2% in the control arm); most cases of HAT occurred within 30 days post-transplantation, and most led to graft loss or death.

In a clinical study in stable liver transplant patients 6–144 months post-liver transplantation and receiving a CNI-based regimen, an increased number of deaths was observed in the group converted to a sirolimus-based regimen compared to the group who was continued on a CNI-based regimen, although the difference was not statistically significant (3.8% versus 1.4%) [ see Clinical Studies (14.5)].

5.3 Lung Transplantation – Bronchial Anastomotic Dehiscence

Cases of bronchial anastomotic dehiscence, most fatal, have been reported in de novolung transplant patients when sirolimus has been used as part of an immunosuppressive regimen.

The safety and efficacy of sirolimus as immunosuppressive therapy have not been established in lung transplant patients; therefore, such use is not recommended.

5.4 Hypersensitivity Reactions

Hypersensitivity reactions, including anaphylactic/anaphylactoid reactions, angioedema, exfoliative dermatitis and hypersensitivity vasculitis, have been associated with the administration of sirolimus [ see Adverse Reactions (6.7)].

5.5 Angioedema

Sirolimus has been associated with the development of angioedema. The concomitant use of sirolimus with other drugs known to cause angioedema, such as angiotensin converting enzyme (ACE) inhibitors, may increase the risk of developing angioedema. Elevated sirolimus levels (with/without concomitant ACE inhibitors) may also potentiate angioedema [ see Drug Interactions (7.2)]. In some cases, the angioedema has resolved upon discontinuation or dose reduction of sirolimus.

5.6 Fluid Accumulation and Impairment of Wound Healing

There have been reports of impaired or delayed wound healing in patients receiving sirolimus, including lymphocele and wound dehiscence [ see Adverse Reactions (6.1)]. Mammalian target of rapamycin (mTOR) inhibitors such as sirolimus have been shown in vitroto inhibit production of certain growth factors that may affect angiogenesis, fibroblast proliferation, and vascular permeability. Lymphocele, a known surgical complication of renal transplantation, occurred significantly more often in a dose-related fashion in patients treated with sirolimus [ see Adverse Reactions (6.1)]. Appropriate measures should be considered to minimize such complications. Patients with a body mass index (BMI) greater than 30 kg/m^2may be at increased risk of abnormal wound healing based on data from the medical literature.

There have also been reports of fluid accumulation, including peripheral edema, lymphedema, pleural effusion, ascites, and pericardial effusions (including hemodynamically significant effusions and tamponade requiring intervention in children and adults), in patients receiving sirolimus.

5.7 Hyperlipidemia

Increased serum cholesterol and triglycerides requiring treatment occurred more frequently in patients treated with sirolimus compared with azathioprine or placebo controls in Studies 1 and 2 [ see Adverse Reactions (6.1)]. There were increased incidences of hypercholesterolemia (43–46%) and/or hypertriglyceridemia (45–57%) in patients receiving sirolimus compared with placebo controls (each 23%). The risk/benefit should be carefully considered in patients with established hyperlipidemia before initiating an immunosuppressive regimen including sirolimus.

Any patient who is administered sirolimus should be monitored for hyperlipidemia. If detected, interventions such as diet, exercise, and lipid-lowering agents should be initiated as outlined by the National Cholesterol Education Program guidelines.

In clinical trials of patients receiving sirolimus plus cyclosporine or sirolimus after cyclosporine withdrawal, up to 90% of patients required treatment for hyperlipidemia and hypercholesterolemia with anti-lipid therapy (e.g., statins, fibrates). Despite anti-lipid management, up to 50% of patients had fasting serum cholesterol levels >240 mg/dL and triglycerides above recommended target levels. The concomitant administration of sirolimus and HMG-CoA reductase inhibitors resulted in adverse reactions such as CPK elevations (3%), myalgia (6.7%) and rhabdomyolysis (<1%). In these trials, the number of patients was too small and duration of follow-up too short to evaluate the long-term impact of sirolimus on cardiovascular mortality.

During sirolimus therapy with or without cyclosporine, patients should be monitored for elevated lipids, and patients administered an HMG-CoA reductase inhibitor and/or fibrate should be monitored for the possible development of rhabdomyolysis and other adverse effects, as described in the respective labeling for these agents.

5.8 Decline in Renal Function

Renal function should be closely monitored during the co-administration of sirolimus with cyclosporine, because long-term administration of the combination has been associated with deterioration of renal function. Patients treated with cyclosporine and sirolimus were noted to have higher serum creatinine levels and lower glomerular filtration rates compared with patients treated with cyclosporine and placebo or azathioprine controls (Studies 1 and 2). The rate of decline in renal function in these studies was greater in patients receiving sirolimus and cyclosporine compared with control therapies.

Appropriate adjustment of the immunosuppressive regimen, including discontinuation of sirolimus and/or cyclosporine, should be considered in patients with elevated or increasing serum creatinine levels. In patients at low- to moderate-immunologic risk, continuation of combination therapy with cyclosporine beyond 4 months following transplantation should only be considered when the benefits outweigh the risks of this combination for the individual patients. Caution should be exercised when using agents (e.g., aminoglycosides and amphotericin B) that are known to have a deleterious effect on renal function.

In patients with delayed graft function, sirolimus may delay recovery of renal function.

5.9 Proteinuria

Periodic quantitative monitoring of urinary protein excretion is recommended. In a study evaluating conversion from calcineurin inhibitors (CNI) to sirolimus in maintenance renal transplant patients 6–120 months post-transplant, increased urinary protein excretion was commonly observed from 6 through 24 months after conversion to sirolimus compared with CNI continuation [ see Clinical Studies (14.4), Adverse Reactions (6.4)]. Patients with the greatest amount of urinary protein excretion prior to sirolimus conversion were those whose protein excretion increased the most after conversion. New onset nephrosis (nephrotic syndrome) was also reported as a treatment-emergent adverse reaction in 2.2% of the sirolimus conversion group patients in comparison to 0.4% in the CNI continuation group of patients. Nephrotic range proteinuria (defined as urinary protein to creatinine ratio >3.5) was also reported in 9.2% in the sirolimus conversion group of patients in comparison to 3.7% in the CNI continuation group of patients. In some patients, reduction in the degree of urinary protein excretion was observed for individual patients following discontinuation of sirolimus. The safety and efficacy of conversion from calcineurin inhibitors to sirolimus in maintenance renal transplant patients have not been established.

5.10 Latent Viral Infections

Immunosuppressed patients are at increased risk for opportunistic infections, including activation of latent viral infections. These include BK virus-associated nephropathy, which has been observed in renal transplant patients receiving immunosuppressants, including sirolimus. This infection may be associated with serious outcomes, including deteriorating renal function and renal graft loss [ see Adverse Reactions (6.7)]. Patient monitoring may help detect patients at risk for BK virus-associated nephropathy. Reduction in immunosuppression should be considered for patients who develop evidence of BK virus-associated nephropathy.

Cases of progressive multifocal leukoencephalopathy (PML), sometimes fatal have been reported in patients treated with immunosuppressants, including sirolimus. PML commonly presents with hemiparesis, apathy, confusion, cognitive deficiencies and ataxia. Risk factors for PML include treatment with immunosuppressant therapies and impairment of immune function. In immunosuppressed patients, physicians should consider PML in the differential diagnosis in patients reporting neurological symptoms and consultation with a neurologist should be considered as clinically indicated. Consideration should be given to reducing the amount of immunosuppression in patients who develop PML. In transplant patients, physicians should also consider the risk that reduced immunosuppression represents to the graft.

5.11 Interstitial Lung Disease/Non-Infectious Pneumonitis

Cases of interstitial lung disease [ILD] (including pneumonitis, bronchiolitis obliterans organizing pneumonia [BOOP], and pulmonary fibrosis), some fatal, with no identified infectious etiology have occurred in patients receiving immunosuppressive regimens including sirolimus. In some cases, the ILD was reported with pulmonary hypertension (including pulmonary arterial hypertension [PAH]) as a secondary event. In some cases, the ILD has resolved upon discontinuation or dose reduction of sirolimus. The risk may be increased as the trough sirolimus concentration increases [ see Adverse Reactions (6.7)].

5.12 De NovoUse Without Cyclosporine

The safety and efficacy of de novouse of sirolimus without cyclosporine is not established in renal transplant patients. In a multicenter clinical study, de novorenal transplant patients treated with sirolimus, mycophenolate mofetil (MMF), steroids, and an IL-2 receptor antagonist had significantly higher acute rejection rates and numerically higher death rates compared to patients treated with cyclosporine, MMF, steroids, and IL-2 receptor antagonist. A benefit, in terms of better renal function, was not apparent in the treatment arm with de novouse of sirolimus without cyclosporine. These findings were also observed in a similar treatment group of another clinical trial.

5.13 Increased Risk of Calcineurin Inhibitor-Induced Hemolytic Uremic Syndrome/Thrombotic Thrombocytopenic Purpura/Thrombotic Microangiopathy

The concomitant use of sirolimus with a calcineurin inhibitor may increase the risk of calcineurin inhibitor-induced hemolytic uremic syndrome/thrombotic thrombocytopenic purpura/thrombotic microangiopathy (HUS/TTP/TMA) [ see Adverse Reactions (6.7)].

5.14 Antimicrobial Prophylaxis

Cases of Pneumocystis cariniipneumonia have been reported in transplant patients not receiving antimicrobial prophylaxis. Therefore, antimicrobial prophylaxis for Pneumocystis cariniipneumonia should be administered for 1 year following transplantation.

Cytomegalovirus (CMV) prophylaxis is recommended for 3 months after transplantation, particularly for patients at increased risk for CMV disease.

5.15 Embryo-Fetal Toxicity

Based on animal studies and the mechanism of action [ see Clinical Pharmacology (12.1)], sirolimus can cause fetal harm when administered to a pregnant woman. In animal studies, sirolimus caused embryo-fetal toxicity when administered during the period of organogenesis at maternal exposures that were equal to or less than human exposures at the recommended lowest starting dose. Advise pregnant women of the potential risk to a fetus. Advise female patients of reproductive potential to avoid becoming pregnant and to use highly effective contraception while using sirolimus and for 12 weeks after ending treatment [ see Use in Specific Populations (8.1)] .

5.16 Male Infertility

Azoospermia or oligospermia may be observed [ see Adverse Reactions (6.7), Nonclinical Toxicology (13.1)] .Sirolimus is an anti-proliferative drug and affects rapidly dividing cells like the germ cells.

5.17 Different Sirolimus Trough Concentration Reported between Chromatographic and Immunoassay Methodologies

Currently in clinical practice, sirolimus whole blood concentrations are being measured by various chromatographic and immunoassay methodologies. Patient sample concentration values from different assays may not be interchangeable [ see Dosage and Administration (2.5)].

5.18 Skin Cancer Events

Patients on immunosuppressive therapy are at increased risk for skin cancer. Exposure to sunlight and ultraviolet (UV) light should be limited by wearing protective clothing and using a broad spectrum sunscreen with a high protection factor [ see Adverse Reactions (6.1, 6.2, 6.7)] .

5.19 Immunizations

The use of live vaccines should be avoided during treatment with sirolimus; live vaccines may include, but are not limited to, the following: measles, mumps, rubella, oral polio, BCG, yellow fever, varicella, and TY21a typhoid. Immunosuppressants may affect response to vaccination. Therefore, during treatment with sirolimus, vaccination may be less effective.

5.20 Interaction with Strong Inhibitors and Inducers of CYP3A4 and/or P-gp

Avoid concomitant use of sirolimus with strong inhibitors of CYP3A4 and/or P-gp (such as ketoconazole, voriconazole, itraconazole, erythromycin, telithromycin, or clarithromycin) or strong inducers of CYP3A4 and/or P-gp (such as rifampin or rifabutin) [ see Drug Interactions (7.2)].

5.21 Cannabidiol Drug Interactions

When cannabidiol and sirolimus are co-administered, closely monitor for an increase in sirolimus blood levels and for adverse reactions suggestive of sirolimus toxicity. A dose reduction of sirolimus should be considered as needed when sirolimus is co-administered with cannabidiol [ see Dosage and Administration (2.5), Drug Interactions (7.5)].

6 ADVERSE REACTIONS

The following adverse reactions are discussed in greater detail in other sections of the label.

- Increased susceptibility to infection, lymphoma, and malignancy [ see Boxed Warning, Warnings and Precautions (5.1)]
- Excess mortality, graft loss, and hepatic artery thrombosis in liver transplant patients [ see Boxed Warning, Warnings and Precautions (5.2)]
- Bronchial anastomotic dehiscence in lung transplant patients [ see Boxed Warning, Warnings and Precautions (5.3)]
- Hypersensitivity reactions [ see Warnings and Precautions (5.4)]
- Exfoliative dermatitis [ see Warnings and Precautions (5.4)]
- Angioedema [ see Warnings and Precautions (5.5)]
- Fluid accumulation and impairment of wound healing [ see Warnings and Precautions (5.6)]
- Hypertriglyceridemia, hypercholesterolemia [ see Warnings and Precautions (5.7)]
- Decline in renal function in long-term combination of cyclosporine with sirolimus [ see Warnings and Precautions (5.8)]
- Proteinuria [ see Warnings and Precautions (5.9)]
- Interstitial lung disease [ see Warnings and Precautions (5.11)]
- Increased risk of calcineurin inhibitor-induced HUS/TTP/TMA [ see Warnings and Precautions (5.13)]
- Embryo-fetal toxicity [ see Warnings and Precautions (5.15)]
- Male infertility [ see Warnings and Precautions (5.16)]

The most common (≥30%) adverse reactions observed with sirolimus in clinical studies for organ rejection prophylaxis in recipients of renal transplantation are: peripheral edema, hypertriglyceridemia, hypertension, hypercholesterolemia, creatinine increased, constipation, abdominal pain, diarrhea, headache, fever, urinary tract infection, anemia, nausea, arthralgia, pain, and thrombocytopenia.

The most common (≥20%) adverse reactions observed with sirolimus in the clinical study for the treatment of LAM are: stomatitis, diarrhea, abdominal pain, nausea, nasopharyngitis, acne, chest pain, peripheral edema, upper respiratory tract infection, headache, dizziness, myalgia, and hypercholesterolemia.

The following adverse reactions resulted in a rate of discontinuation of >5% in clinical trials for renal transplant rejection prophylaxis: creatinine increased, hypertriglyceridemia, and TTP. In patients with LAM, 11% of subjects discontinued due to adverse reactions, with no single adverse reaction leading to discontinuation in more than one patient being treated with sirolimus.

6.1 Clinical Studies Experience in Prophylaxis of Organ Rejection Following Renal Transplantation

The safety and efficacy of sirolimus oral solution for the prevention of organ rejection following renal transplantation were assessed in two randomized, double-blind, multicenter, controlled trials [ see Clinical Studies (14.1)]. The safety profiles in the two studies were similar.

The incidence of adverse reactions in the randomized, double-blind, multicenter, placebo-controlled trial (Study 2) in which 219 renal transplant patients received sirolimus oral solution 2 mg/day, 208 received sirolimus oral solution 5 mg/day, and 124 received placebo is presented in Table 1 below. The study population had a mean age of 46 years (range 15 to 71 years), the distribution was 67% male, and the composition by race was: White (78%), Black (11%), Asian (3%), Hispanic (2%), and Other (5%). All patients were treated with cyclosporine and corticosteroids. Data (≥ 12 months post-transplant) presented in the following table show the adverse reactions that occurred in at least one of the sirolimus treatment groups with an incidence of ≥20%.

The safety profile of the tablet did not differ from that of the oral solution formulation [ see Clinical Studies (14.1)].

In general, adverse reactions related to the administration of sirolimus were dependent on dose/concentration. Although a daily maintenance dose of 5 mg, with a loading dose of 15 mg, was shown to be safe and effective, no efficacy advantage over the 2 mg dose could be established for renal transplant patients. Patients receiving 2 mg of sirolimus oral solution per day demonstrated an overall better safety profile than did patients receiving 5 mg of sirolimus oral solution per day.

Because clinical trials are conducted under widely varying conditions, adverse reaction rates observed in one clinical trial of a drug cannot be directly compared with rates in the clinical trials of the same or another drug and may not reflect the rates observed in practice.

TABLE 1: ADVERSE REACTIONS OCCURRING AT A FREQUENCY OF ≥20% IN AT LEAST ONE OF THE SIROLIMUS TREATMENT GROUPS IN A STUDY OF PROPHYLAXIS OF ORGAN REJECTION FOLLOWING RENAL TRANSPLANTATION (%) AT ≥ 12 MONTHS POST-TRANSPLANTATION (STUDY 2) [Patients received cyclosporine and corticosteroids.]
 | ––– Sirolimus Oral Solution–––
 | 2 mg/day | 5 mg/day | Placebo
Adverse Reaction | (n = 218) | (n = 208) | (n = 124)
Peripheral edema | 54 | 58 | 48
Hypertriglyceridemia | 45 | 57 | 23
Hypertension | 45 | 49 | 48
Hypercholesterolemia | 43 | 46 | 23
Creatinine increased | 39 | 40 | 38
Constipation | 36 | 38 | 31
Abdominal pain | 29 | 36 | 30
Diarrhea | 25 | 35 | 27
Headache | 34 | 34 | 31
Fever | 23 | 34 | 35
Urinary tract infection | 26 | 33 | 26
Anemia | 23 | 33 | 21
Nausea | 25 | 31 | 29
Arthralgia | 25 | 31 | 18
Thrombocytopenia | 14 | 30 | 9
Pain | 33 | 29 | 25
Acne | 22 | 22 | 19
Rash | 10 | 20 | 6
Edema | 20 | 18 | 15

The following adverse reactions were reported less frequently (≥3%, but <20%)

- Body as a Whole– Sepsis, lymphocele, herpes zoster, herpes simplex.
- Cardiovascular– Venous thromboembolism (including pulmonary embolism, deep venous thrombosis), tachycardia.
- Digestive System– Stomatitis.
- Hematologic and Lymphatic System– Thrombotic thrombocytopenic purpura/hemolytic uremic syndrome (TTP/HUS), leukopenia.
- Metabolic/Nutritional– Abnormal healing, increased lactic dehydrogenase (LDH), hypokalemia, diabetes mellitus.
- Musculoskeletal System– Bone necrosis.
- Respiratory System– Pneumonia, epistaxis.
- Skin– Melanoma, squamous cell carcinoma, basal cell carcinoma.
- Urogenital System– Pyelonephritis, decline in renal function (creatinine increased) in long-term combination of cyclosporine with sirolimus [ see Warnings and Precautions (5.8)], ovarian cysts, menstrual disorders (including amenorrhea and menorrhagia).

Less frequently (<3%) occurring adverse reactions included: lymphoma/post-transplant lymphoproliferative disorder, mycobacterial infections (including M. tuberculosis), pancreatitis, cytomegalovirus (CMV), and Epstein-Barr virus.

Increased Serum Cholesterol and Triglycerides

The use of sirolimus in renal transplant patients was associated with increased serum cholesterol and triglycerides that may require treatment.

In Studies 1 and 2, in de novorenal transplant patients who began the study with fasting, total serum cholesterol <200 mg/dL or fasting, total serum triglycerides <200 mg/dL, there was an increased incidence of hypercholesterolemia (fasting serum cholesterol >240 mg/dL) or hypertriglyceridemia (fasting serum triglycerides >500 mg/dL), respectively, in patients receiving both sirolimus 2 mg and sirolimus 5 mg compared with azathioprine and placebo controls.

Treatment of new-onset hypercholesterolemia with lipid-lowering agents was required in 42–52% of patients enrolled in the sirolimus arms of Studies 1 and 2 compared with 16% of patients in the placebo arm and 22% of patients in the azathioprine arm. In other sirolimus renal transplant studies, up to 90% of patients required treatment for hyperlipidemia and hypercholesterolemia with anti-lipid therapy (e.g., statins, fibrates). Despite anti-lipid management, up to 50% of patients had fasting serum cholesterol levels >240 mg/dL and triglycerides above recommended target levels [ see Warnings and Precautions (5.7)].

Abnormal Healing

Abnormal healing events following transplant surgery include fascial dehiscence, incisional hernia, and anastomosis disruption (e.g., wound, vascular, airway, ureteral, biliary).

Malignancies

Table 2 below summarizes the incidence of malignancies in the two controlled trials (Studies 1 and 2) for the prevention of acute rejection [ see Clinical Studies (14.1)].

At 24 months (Study 1) and 36 months (Study 2) post-transplant, there were no significant differences among treatment groups.

TABLE 2: INCIDENCE (%) OF MALIGNANCIES IN STUDY 1 (24 MONTHS) AND STUDY 2 (36 MONTHS) POST-TRANSPLANT [Patients received cyclosporine and corticosteroids.] , [Includes patients who prematurely discontinued treatment.]
 | Sirolimus Oral Solution 2 mg/day |  | Sirolimus Oral Solution 5 mg/day |  | Azathioprine 2–3 mg/kg/day | Placebo
Malignancy | Study 1 (n = 284) | Study 2 (n = 227) | Study 1 (n = 274) | Study 2 (n = 219) | Study 1 (n = 161) | Study 2 (n = 130)
Lymphoma/lymphoproliferative disease | 0.7 | 1.8 | 1.1 | 3.2 | 0.6 | 0.8
Skin Carcinoma
Any Squamous Cell [Patients may be counted in more than one category.] | 0.4 | 2.7 | 2.2 | 0.9 | 3.8 | 3.0
Any Basal Cell | 0.7 | 2.2 | 1.5 | 1.8 | 2.5 | 5.3
Melanoma | 0.0 | 0.4 | 0.0 | 1.4 | 0.0 | 0.0
Miscellaneous/Not Specified | 0.0 | 0.0 | 0.0 | 0.0 | 0.0 | 0.8
Total | 1.1 | 4.4 | 3.3 | 4.1 | 4.3 | 7.7
Other Malignancy | 1.1 | 2.2 | 1.5 | 1.4 | 0.6 | 2.3

6.2 Sirolimus Following Cyclosporine Withdrawal

The incidence of adverse reactions was determined through 36 months in a randomized, multicenter, controlled trial (Study 3) in which 215 renal transplant patients received sirolimus as a maintenance regimen following cyclosporine withdrawal, and 215 patients received sirolimus with cyclosporine therapy [ see Clinical Studies (14.2)]. All patients were treated with corticosteroids. The safety profile prior to randomization (start of cyclosporine withdrawal) was similar to that of the 2 mg sirolimus groups in Studies 1 and 2.

Following randomization (at 3 months), patients who had cyclosporine eliminated from their therapy experienced higher incidences of the following adverse reactions: abnormal liver function tests (including increased AST/SGOT and increased ALT/SGPT), hypokalemia, thrombocytopenia, and abnormal healing. Conversely, the incidence of the following adverse events was higher in patients who remained on cyclosporine than those who had cyclosporine withdrawn from therapy: hypertension, cyclosporine toxicity, increased creatinine, abnormal kidney function, toxic nephropathy, edema, hyperkalemia, hyperuricemia, and gum hyperplasia. Mean systolic and diastolic blood pressure improved significantly following cyclosporine withdrawal.

Malignancies

The incidence of malignancies in Study 3 [ see Clinical Studies (14.2)] is presented in Table 3.

In Study 3, the incidence of lymphoma/lymphoproliferative disease was similar in all treatment groups. The overall incidence of malignancy was higher in patients receiving sirolimus plus cyclosporine compared with patients who had cyclosporine withdrawn. Conclusions regarding these differences in the incidence of malignancy could not be made because Study 3 was not designed to consider malignancy risk factors or systematically screen subjects for malignancy. In addition, more patients in the sirolimus with cyclosporine group had a pre-transplantation history of skin carcinoma.

TABLE 3: INCIDENCE (%) OF MALIGNANCIES IN STUDY 3 (CYCLOSPORINE WITHDRAWAL STUDY) AT 36 MONTHS POST-TRANSPLANT [Patients received cyclosporine and corticosteroids.] , [Includes patients who prematurely discontinued treatment.]
Malignancy | Nonrandomized (n = 95) | Sirolimus with Cyclosporine Therapy (n = 215) | Sirolimus Following Cyclosporine Withdrawal (n = 215)
Lymphoma/lymphoproliferative disease | 1.1 | 1.4 | 0.5
Skin Carcinoma
Any Squamous Cell [Patients may be counted in more than one category.] | 3.2 | 3.3 | 2.3
Any Basal Cell | 3.2 | 6.5 | 2.3
Melanoma | 0.0 | 0.5 | 0.0
Miscellaneous/Not Specified | 1.1 | 0.9 | 0.0
Total | 4.2 | 7.9 | 3.7
Other Malignancy | 3.2 | 3.3 | 1.9

6.3 High-Immunologic Risk Renal Transplant Patients

Safety was assessed in 224 patients who received at least one dose of sirolimus with cyclosporine [ see Clinical Studies (14.3)]. Overall, the incidence and nature of adverse reactions was similar to those seen in previous combination studies with sirolimus. The incidence of malignancy was 1.3% at 12 months.

6.4 Conversion from Calcineurin Inhibitors to Sirolimus in Maintenance Renal Transplant Population

The safety and efficacy of conversion from calcineurin inhibitors to sirolimus in maintenance renal transplant population have not been established [ see Clinical Studies (14.4)]. In a study evaluating the safety and efficacy of conversion from calcineurin inhibitors to sirolimus (initial target sirolimus concentrations of 12–20 ng/mL, and then 8–20 ng/mL, by chromatographic assay) in maintenance renal transplant patients, enrollment was stopped in the subset of patients (n = 87) with a baseline glomerular filtration rate of less than 40 mL/min. There was a higher rate of serious adverse events, including pneumonia, acute rejection, graft loss and death, in this stratum of the sirolimus treatment arm.

The subset of patients with a baseline glomerular filtration rate of less than 40 mL/min had 2 years of follow-up after randomization. In this population, the rate of pneumonia was 25.9% (15/58) versus 13.8% (4/29), graft loss (excluding death with functioning graft loss) was 22.4% (13/58) versus 31.0% (9/29), and death was 15.5% (9/58) versus 3.4% (1/29) in the sirolimus conversion group and CNI continuation group, respectively.

In the subset of patients with a baseline glomerular filtration rate of greater than 40 mL/min, there was no benefit associated with conversion with regard to improvement in renal function and a greater incidence of proteinuria in the sirolimus conversion arm.

Overall in this study, a 5-fold increase in the reports of tuberculosis among sirolimus 2.0% (11/551) and comparator 0.4% (1/273) treatment groups was observed with 2:1 randomization scheme.

In a second study evaluating the safety and efficacy of conversion from tacrolimus to sirolimus 3 to 5 months post-kidney transplant, a higher rate of adverse events, discontinuations due to adverse events, acute rejection, and new onset diabetes mellitus was observed following conversion to sirolimus. There was also no benefit with respect to renal function and a greater incidence of proteinuria was observed after conversion to sirolimus [(see Clinical Studies (14.4)] .

6.5 Pediatric Renal Transplant Patients

Safety was assessed in a controlled clinical trial in pediatric (<18 years of age) renal transplant patients considered at high-immunologic risk, defined as a history of one or more acute allograft rejection episodes and/or the presence of chronic allograft nephropathy on a renal biopsy [ see Clinical Studies (14.6)]. The use of sirolimus in combination with calcineurin inhibitors and corticosteroids was associated with a higher incidence of deterioration of renal function (creatinine increased) compared to calcineurin inhibitor-based therapy, serum lipid abnormalities (including, but not limited to, increased serum triglycerides and cholesterol), and urinary tract infections.

6.6 Patients with Lymphangioleiomyomatosis

Safety was assessed in a controlled trial involving 89 patients with lymphangioleiomyomatosis, 46 of whom were treated with sirolimus [ see Clinical Studies (14.7)]. The adverse drug reactions observed in this trial were consistent with the known safety profile for renal transplant patients receiving sirolimus, with the addition of weight decreased which was reported at a greater incidence with sirolimus when compared to placebo. Adverse reactions occurring at a frequency of ≥20% in the sirolimus treatment group and greater than placebo include stomatitis, diarrhea, abdominal pain, nausea, nasopharyngitis, acne, chest pain, peripheral edema, upper respiratory tract infection, headache, dizziness, myalgia, and hypercholesterolemia.

6.7 Postmarketing Experience

The following adverse reactions have been identified during post-approval use of sirolimus in transplant patients. Because these reactions are reported voluntarily from a population of uncertain size, it is not always possible to reliably estimate their frequency or establish a causal relationship to drug exposure.

- Body as a Whole– Lymphedema.
- Cardiovascular– Pericardial effusion (including hemodynamically significant effusions and tamponade requiring intervention in children and adults) and fluid accumulation.
- Digestive System– Ascites.
- Hematological/Lymphatic– Pancytopenia, neutropenia.
- Hepatobiliary Disorders– Hepatotoxicity, including fatal hepatic necrosis, with elevated sirolimus trough concentrations.
- Immune System– Hypersensitivity reactions, including anaphylactic/anaphylactoid reactions, angioedema, and hypersensitivity vasculitis [ see Warnings and Precautions (5.4)].
- Infections– Tuberculosis. BK virus associated nephropathy has been observed in patients receiving immunosuppressants, including sirolimus. This infection may be associated with serious outcomes, including deteriorating renal function and renal graft loss. Cases of progressive multifocal leukoencephalopathy (PML), sometimes fatal, have been reported in patients treated with immunosuppressants, including sirolimus [ see Warnings and Precautions (5.10)]. Clostridium difficileenterocolitis.
- Metabolic/Nutritional– Liver function test abnormal, AST/SGOT increased, ALT/SGPT increased, hypophosphatemia, hyperglycemia, diabetes mellitus.
- Nervous System- Posterior reversible encephalopathy syndrome.
- Respiratory– Cases of interstitial lung disease (including pneumonitis, bronchiolitis obliterans organizing pneumonia [BOOP], and pulmonary fibrosis), some fatal, with no identified infectious etiology have occurred in patients receiving immunosuppressive regimens including sirolimus. In some cases, the interstitial lung disease has resolved upon discontinuation or dose reduction of sirolimus. The risk may be increased as the sirolimus trough concentration increases [ see Warnings and Precautions (5.11)]; pulmonary hemorrhage; pleural effusion; alveolar proteinosis.
- Skin– Neuroendocrine carcinoma of the skin (Merkel cell carcinoma) [ see Warnings and Precautions (5.18)] ,exfoliative dermatitis [ see Warnings and Precautions (5.4)].
- Urogenital– Nephrotic syndrome, proteinuria, focal segmental glomerulosclerosis, ovarian cysts, menstrual disorders (including amenorrhea and menorrhagia). Azoospermia has been reported with the use of sirolimus and has been reversible upon discontinuation of sirolimus in most cases.

7 DRUG INTERACTIONS

Sirolimus is known to be a substrate for both cytochrome P-450 3A4 (CYP3A4) and p-glycoprotein (P-gp). Inducers of CYP3A4 and P-gp may decrease sirolimus concentrations whereas inhibitors of CYP3A4 and P-gp may increase sirolimus concentrations.

7.1 Use with Cyclosporine

Cyclosporine, a substrate and inhibitor of CYP3A4 and P-gp, was demonstrated to increase sirolimus concentrations when co-administered with sirolimus. In order to diminish the effect of this interaction with cyclosporine, it is recommended that sirolimus be taken 4 hours after administration of cyclosporine oral solution (MODIFIED) and/or cyclosporine capsules (MODIFIED). If cyclosporine is withdrawn from combination therapy with sirolimus, higher doses of sirolimus are needed to maintain the recommended sirolimus trough concentration ranges [ see Dosage and Administration (2.2), Clinical Pharmacology (12.3)].

7.2 Strong Inducers and Strong Inhibitors of CYP3A4 and P-gp

Avoid concomitant use of sirolimus with strong inducers (e.g., rifampin, rifabutin) and strong inhibitors (e.g., ketoconazole, voriconazole, itraconazole, erythromycin, telithromycin, clarithromycin) of CYP3A4 and P-gp. Alternative agents with lesser interaction potential with sirolimus should be considered [ see Warnings and Precautions (5.20), Clinical Pharmacology (12.3)].

7.3 Grapefruit Juice

Because grapefruit juice inhibits the CYP3A4-mediated metabolism of sirolimus, it must not be taken with sirolimus [ see Clinical Pharmacology (12.3)].

7.4 Weak and Moderate Inducers or Inhibitors of CYP3A4 and P-gp

Exercise caution when using sirolimus with drugs or agents that are modulators of CYP3A4 and P-gp. The dosage of sirolimus and/or the co-administered drug may need to be adjusted [ see Clinical Pharmacology (12.3)].

- Drugs that could increase sirolimus blood concentrations:
  Bromocriptine, cimetidine, cisapride, clotrimazole, danazol, diltiazem, fluconazole, letermovir, protease inhibitors (e.g., HIV and hepatitis C that include drugs such as ritonavir, indinavir, boceprevir, and telaprevir), metoclopramide, nicardipine, troleandomycin, verapamil
- Drugs and other agents that could decrease sirolimus concentrations:
  Carbamazepine, phenobarbital, phenytoin, rifapentine, St. John's Wort (Hypericum perforatum)
- Drugs with concentrations that could increase when given with sirolimus:
  Verapamil

7.5 Cannabidiol

The blood levels of sirolimus may increase upon concomitant use with cannabidiol. When cannabidiol and sirolimus are co-administered, closely monitor for an increase in sirolimus blood levels and for adverse reactions suggestive of sirolimus toxicity. A dose reduction of sirolimus should be considered as needed when sirolimus is co-administered with cannabidiol [ see Dosage and Administration (2.5), Warnings and Precautions (5.21)].

8 USE IN SPECIFIC POPULATIONS

8.1 Pregnancy

Risk Summary

Based on animal studies and the mechanism of action, sirolimus can cause fetal harm when administered to a pregnant woman [ see Data, Clinical Pharmacology (12.1)]. There are limited data on the use of sirolimus during pregnancy; however, these data are insufficient to inform a drug-associated risk of adverse developmental outcomes. In animal studies, sirolimus was embryo/fetotoxic in rats at sub-therapeutic doses [ see Data]. Advise pregnant women of the potential risk to a fetus.

The estimated background risk of major birth defects and miscarriage for the indicated population is unknown. In the U.S. general population, the estimated background risk of major birth defects and miscarriage in clinically recognized pregnancies is 2–4% and 15–20%, respectively.

Data

Animal Data

Sirolimus crossed the placenta and was toxic to the conceptus.

In rat embryo-fetal development studies, pregnant rats were administered sirolimus orally during the period of organogenesis (Gestational Day 6–15). Sirolimus produced embryo-fetal lethality at 0.5 mg/kg (2.5-fold the clinical dose of 2 mg, on a body surface area basis) and reduced fetal weight at 1 mg/kg (5-fold the clinical dose of 2 mg). The no observed adverse effect level (NOAEL) for fetal toxicity in rats was 0.1 mg/kg (0.5-fold the clinical dose of 2 mg). Maternal toxicity (weight loss) was observed at 2 mg/kg (10-fold the clinical dose of 2 mg). The NOAEL for maternal toxicity was 1 mg/kg. In combination with cyclosporine, rats had increased embryo-fetal mortality compared with sirolimus alone.

In rabbit embryo-fetal development studies, pregnant rabbits were administered sirolimus orally during the period of organogenesis (Gestational Day 6–18). There were no effects on embryo-fetal development at doses up to 0.05 mg/kg (0.5-fold the clinical dose of 2 mg, on a body surface area basis); however, at doses of 0.05 mg/kg and above, the ability to sustain a successful pregnancy was impaired (i.e., embryo-fetal abortion or early resorption). Maternal toxicity (decreased body weight) was observed at 0.05 mg/kg. The NOAEL for maternal toxicity was 0.025 mg/kg (0.25-fold the clinical dose of 2 mg).

In a pre- and post-natal development study in rats, pregnant females were dosed during gestation and lactation (Gestational Day 6 through Lactation Day 20). An increased incidence of dead pups, resulting in reduced live litter size, occurred at 0.5 mg/kg (2.5-fold the clinical dose of 2 mg/kg on a body surface area basis). At 0.1 mg/kg (0.5-fold the clinical dose of 2 mg), there were no adverse effects on offspring. Sirolimus did not cause maternal toxicity or affect developmental parameters in the surviving offspring (morphological development, motor activity, learning, or fertility assessment) at 0.5 mg/kg, the highest dose tested.

8.2 Lactation

Risk Summary

It is not known whether sirolimus is present in human milk. There are no data on its effects on the breastfed infant or milk production. The pharmacokinetic and safety profiles of sirolimus in infants are not known. Sirolimus is present in the milk of lactating rats. There is potential for serious adverse effects from sirolimus in breastfed infants based on mechanism of action [ see Clinical Pharmacology (12.1)] .The developmental and health benefits of breastfeeding should be considered along with the mother's clinical need for sirolimus and any potential adverse effects on the breastfed child from sirolimus.

8.3 Females and Males of Reproductive Potential

Contraception

Females should not be pregnant or become pregnant while receiving sirolimus. Advise females of reproductive potential that animal studies have been shown sirolimus to be harmful to the developing fetus. Females of reproductive potential are recommended to use highly effective contraceptive method. Effective contraception must be initiated before sirolimus therapy, during sirolimus therapy, and for 12 weeks after sirolimus therapy has been stopped [ see Warnings and Precautions (5.15), Use in Specific Populations (8.1)].

Infertility

Based on clinical findings and findings in animals, male and female fertility may be compromised by the treatment with sirolimus [ see Adverse Reactions (6.7), Nonclinical Toxicology (13.1)]. Ovarian cysts and menstrual disorders (including amenorrhea and menorrhagia) have been reported in females with the use of sirolimus. Azoospermia has been reported in males with the use of sirolimus and has been reversible upon discontinuation of sirolimus in most cases.

8.4 Pediatric Use

Renal Transplant

The safety and efficacy of sirolimus in pediatric patients <13 years have not been established.

The safety and efficacy of sirolimus oral solution and sirolimus tablets have been established for prophylaxis of organ rejection in renal transplantation in children ≥13 years judged to be at low- to moderate-immunologic risk. Use of sirolimus oral solution and sirolimus tablets in this subpopulation of children ≥13 years is supported by evidence from adequate and well-controlled trials of sirolimus oral solution in adults with additional pharmacokinetic data in pediatric renal transplantation patients [ see Clinical Pharmacology (12.3)].

Safety and efficacy information from a controlled clinical trial in pediatric and adolescent (<18 years of age) renal transplant patients judged to be at high-immunologic risk, defined as a history of one or more acute rejection episodes and/or the presence of chronic allograft nephropathy, do not support the chronic use of sirolimus oral solution or tablets in combination with calcineurin inhibitors and corticosteroids, due to the higher incidence of lipid abnormalities and deterioration of renal function associated with these immunosuppressive regimens compared to calcineurin inhibitors, without increased benefit with respect to acute rejection, graft survival, or patient survival [ see Clinical Studies (14.6)].

Lymphangioleiomyomatosis

The safety and efficacy of Sirolimus in pediatric patients <18 years have not been established.

8.5 Geriatric Use

Clinical studies of sirolimus oral solution or tablets did not include sufficient numbers of patients ≥65 years to determine whether they respond differently from younger patients. Data pertaining to sirolimus trough concentrations suggest that dose adjustments based upon age in geriatric renal patients are not necessary. Differences in responses between the elderly and younger patients have not been identified. In general, dose selection for an elderly patient should be cautious, usually starting at the low end of the dosing range, reflecting the greater frequency of decreased hepatic, or cardiac function, and of concomitant disease or other drug therapy.

8.6 Patients with Hepatic Impairment

The maintenance dose of sirolimus should be reduced in patients with hepatic impairment [ see Dosage and Administration (2.7), Clinical Pharmacology (12.3)].

8.7 Patients with Renal Impairment

Dosage adjustment is not required in patients with renal impairment [ see Dosage and Administration (2.8), Clinical Pharmacology (12.3)].

10 OVERDOSAGE

Reports of overdose with sirolimus have been received; however, experience has been limited. In general, the adverse effects of overdose are consistent with those listed in the adverse reactions section [ see Adverse Reactions (6)].

General supportive measures should be followed in all cases of overdose. Based on the low aqueous solubility and high erythrocyte and plasma protein binding of sirolimus, it is anticipated that sirolimus is not dialyzable to any significant extent. In mice and rats, the acute oral LD50was greater than 800 mg/kg.

11 DESCRIPTION

Sirolimus is an mTOR inhibitor immunosuppressive agent. Sirolimus is a macrocyclic lactone produced by Streptomyces hygroscopicus. The chemical name of sirolimus (also known as rapamycin) is (3 S,6 R,7 E,9 R,10 R,12 R,14 S,15 E,17 E,19 E,21 S,23 S,26 R,27 R,34a S)-9,10,12,13,14,21,22,23,24,25,26,27,32,33,34, 34a-hexadecahydro-9,27-dihydroxy-3-[(1 R)-2-[(1 S,3 R,4 R)-4-hydroxy-3-methoxycyclohexyl]-1-methylethyl]-10,21-dimethoxy-6,8,12,14,20,26-hexamethyl-23,27-epoxy-3 H-pyrido[2,1-c][1,4] oxaazacyclohentriacontine-1,5,11,28,29 (4 H,6 H,31 H)-pentone. Its molecular formula is C51H79NO13and its molecular weight is 914.2. The structural formula of sirolimus is illustrated as follows.

Sirolimus is a white to off-white powder and is insoluble in water, but freely soluble in benzyl alcohol, chloroform, acetone, and acetonitrile.

Sirolimus is available as a tan, triangular-shaped tablet containing 0.5 mg sirolimus, as a white, triangular-shaped tablet containing 1 mg sirolimus, and as a yellow-to-beige triangular-shaped tablet containing 2 mg sirolimus.

The inactive ingredients in sirolimus tablets include sucrose, lactose, polyethylene glycol 8000, calcium sulfate, microcrystalline cellulose, pharmaceutical glaze, talc, titanium dioxide, magnesium stearate, povidone, poloxamer 188, polyethylene glycol 20,000, glyceryl monooleate, carnauba wax, dl-alpha tocopherol, and other ingredients. The 0.5 mg and 2 mg dosage strengths also contain yellow iron (ferric) oxide and brown iron (ferric) oxide.

12 CLINICAL PHARMACOLOGY

12.1 Mechanism of Action

Sirolimus inhibits T-lymphocyte activation and proliferation that occurs in response to antigenic and cytokine (Interleukin [IL]-2, IL-4, and IL-15) stimulation by a mechanism that is distinct from that of other immunosuppressants. Sirolimus also inhibits antibody production. In cells, sirolimus binds to the immunophilin, FK Binding Protein-12 (FKBP-12), to generate an immunosuppressive complex. The sirolimus:FKBP-12 complex has no effect on calcineurin activity. This complex binds to and inhibits the activation of the mammalian target of rapamycin (mTOR), a key regulatory kinase. This inhibition suppresses cytokine-driven T-cell proliferation, inhibiting the progression from the G1to the S phase of the cell cycle.

Mammalian target of rapamycin (mTOR) inhibitors such as sirolimus have been shown in vitroto inhibit production of certain growth factors that may affect angiogenesis, fibroblast proliferation, and vascular permeability.

Studies in experimental models show that sirolimus prolongs allograft (kidney, heart, skin, islet, small bowel, pancreatico-duodenal, and bone marrow) survival in mice, rats, pigs, and/or primates. Sirolimus reverses acute rejection of heart and kidney allografts in rats and prolongs the graft survival in presensitized rats. In some studies, the immunosuppressive effect of sirolimus lasts up to 6 months after discontinuation of therapy. This tolerization effect is alloantigen-specific.

In rodent models of autoimmune disease, sirolimus suppresses immune-mediated events associated with systemic lupus erythematosus, collagen-induced arthritis, autoimmune type I diabetes, autoimmune myocarditis, experimental allergic encephalomyelitis, graft-versus-host disease, and autoimmune uveoretinitis.

Lymphangioleiomyomatosis involves lung tissue infiltration with smooth muscle-like cells that harbor inactivating mutations of the tuberous sclerosis complex (TSC) gene (LAM cells). Loss of TSC gene function activates the mTOR signaling pathway, resulting in cellular proliferation and release of lymphangiogenic growth factors. Sirolimus inhibits the activated mTOR pathway and thus the proliferation of LAM cells.

12.2 Pharmacodynamics

Orally-administered sirolimus, at doses of 2 mg/day and 5 mg/day, significantly reduced the incidence of organ rejection in low-to moderate-immunologic risk renal transplant patients at 6 months following transplantation compared with either azathioprine or placebo [ see Clinical Studies (14.1)]. There was no demonstrable efficacy advantage of a daily maintenance dose of 5 mg with a loading dose of 15 mg over a daily maintenance dose of 2 mg with a loading dose of 6 mg. Therapeutic drug monitoring should be used to maintain sirolimus drug levels within the target-range [ see Dosage and Administration (2.5)].

12.3 Pharmacokinetics

Sirolimus pharmacokinetics activity have been determined following oral administration in healthy subjects, pediatric patients, hepatically impaired patients, and renal transplant patients.

The pharmacokinetic parameters of sirolimus in low- to moderate-immunologic risk adult renal transplant patients following multiple dosing with sirolimus 2 mg daily, in combination with cyclosporine and corticosteroids, is summarized in Table 4.

TABLE 4: MEAN ± SD STEADY STATE SIROLIMUS PHARMACOKINETIC PARAMETERS IN LOW- TO MODERATE-IMMUNOLOGIC RISK ADULT RENAL TRANSPLANT PATIENTS FOLLOWING SIROLIMUS 2 MG DAILY [In presence of cyclosporine administered 4 hours before sirolimus dosing.] , [Based on data collected at months 1 and 3 post-transplantation.]
 | Multiple Dose (daily dose)
 | Solution | Tablets
Cmax(ng/mL) | 14.4 ± 5.3 | 15.0 ± 4.9
tmax(hr) | 2.1 ± 0.8 | 3.5 ± 2.4
AUC (ng∙h/mL) | 194 ± 78 | 230 ± 67
Cmin(ng/mL) [Average C min over 6 months.] | 7.1 ± 3.5 | 7.6 ± 3.1
CL/F (mL/h/kg) | 173 ± 50 | 139 ± 63

Whole blood trough sirolimus concentrations, as measured by LC/MS/MS in renal transplant patients, were significantly correlated with AUCτ,ss. Upon repeated, twice-daily administration without an initial loading dose in a multiple-dose study, the average trough concentration of sirolimus increases approximately 2- to 3-fold over the initial 6 days of therapy, at which time steady-state is reached. A loading dose of 3 times the maintenance dose will provide near steady-state concentrations within 1 day in most patients [ see Dosage and Administration (2.3, 2.5), Warning and Precautions (5.17)].

Absorption

Following administration of sirolimus oral solution, the mean times to peak concentration (tmax) of sirolimus are approximately 1 hour and 2 hours in healthy subjects and renal transplant patients, respectively. The systemic availability of sirolimus is low, and was estimated to be approximately 14% after the administration of sirolimus oral solution. In healthy subjects, the mean bioavailability of sirolimus after administration of the tablet is approximately 27% higher relative to the solution. Sirolimus tablets are not bioequivalent to the solution; however, clinical equivalence has been demonstrated at the 2 mg dose level. Sirolimus concentrations, following the administration of sirolimus oral solution to stable renal transplant patients, are dose-proportional between 3 and 12 mg/m^2.

Food Effects

To minimize variability in sirolimus concentrations, both sirolimus oral solution and tablets should be taken consistently with or without food [ see Dosage and Administration (2)]. In healthy subjects, a high-fat meal (861.8 kcal, 54.9% kcal from fat) increased the mean total exposure (AUC) of sirolimus by 23 to 35%, compared with fasting. The effect of food on the mean sirolimus Cmaxwas inconsistent depending on the sirolimus dosage form evaluated.

Distribution

The mean (± SD) blood-to-plasma ratio of sirolimus was 36 ± 18 in stable renal allograft patients, indicating that sirolimus is extensively partitioned into formed blood elements. The mean volume of distribution (Vss/F) of sirolimus is 12 ± 8 L/kg. Sirolimus is extensively bound (approximately 92%) to human plasma proteins, mainly serum albumin (97%), α1-acid glycoprotein, and lipoproteins.

Metabolism

Sirolimus is a substrate for both CYP3A4 and P-gp. Sirolimus is extensively metabolized in the intestinal wall and liver and undergoes counter-transport from enterocytes of the small intestine into the gut lumen. Inhibitors of CYP3A4 and P-gp increase sirolimus concentrations. Inducers of CYP3A4 and P-gp decrease sirolimus concentrations [ see Warnings and Precautions (5.20)and Drug Interactions (7)]. Sirolimus is extensively metabolized by O-demethylation and/or hydroxylation. Seven (7) major metabolites, including hydroxy, demethyl, and hydroxydemethyl, are identifiable in whole blood. Some of these metabolites are also detectable in plasma, fecal, and urine samples. Sirolimus is the major component in human whole blood and contributes to more than 90% of the immunosuppressive activity.

Excretion

After a single dose of [^14C] sirolimus oral solution in healthy volunteers, the majority (91%) of radioactivity was recovered from the feces, and only a minor amount (2.2%) was excreted in urine. The mean ± SD terminal elimination half-life (t½) of sirolimus after multiple dosing in stable renal transplant patients was estimated to be about 62 ± 16 hours.

Sirolimus Concentrations (Chromatographic Equivalent) Observed in Phase 3 Clinical Studies

The following sirolimus concentrations (chromatographic equivalent) were observed in phase 3 clinical studies for prophylaxis of organ rejection in de novorenal transplant patients [ see Clinical Studies (14)].

TABLE 5: SIROLIMUS WHOLE BLOOD TROUGH CONCENTRATIONS OBSERVED IN RENAL TRANSPLANT PATIENTS ENROLLED IN PHASE 3 STUDIES
Patient Population (Study number) | Treatment | Year 1 |  | Year 3
Patient Population (Study number) | Treatment | Mean (ng/mL) | 10th– 90thpercentiles (ng/mL) | Mean (ng/mL) | 10th– 90thpercentiles (ng/mL)
Low-to-moderate risk (Studies 1 & 2) | Sirolimus (2 mg/day) + CsA | 7.2 | 3.6 – 11 | – | –
Low-to-moderate risk (Studies 1 & 2) | Sirolimus (5 mg/day) + CsA | 14 | 8 – 22 | – | –
Low-to-moderate risk (Study 3) | Sirolimus + CsA | 8.6 | 5 – 13 [Months 4 through 12] | 9.1 | 5.4 – 14
Low-to-moderate risk (Study 3) | Sirolimus alone | 19 | 14 – 22 | 16 | 11 – 22
High risk (Study 4) | Sirolimus + CsA | 15.7 | 5.4 – 27.3 [Up to Week 2; observed CsA C min was 217 (56 – 432) ng/mL] | – | –
High risk (Study 4) |  | 11.8 | 6.2 – 16.9 [Week 2 to Week 26; observed CsA C min range was 174 (71 – 288) ng/mL]
 |  | 11.5 | 6.3 – 17.3 [Week 26 to Week 52; observed CsA C min was 136 (54.5 – 218) ng/mL]

The withdrawal of cyclosporine and concurrent increases in sirolimus trough concentrations to steady-state required approximately 6 weeks. Following cyclosporine withdrawal, larger sirolimus doses were required due to the absence of the inhibition of sirolimus metabolism and transport by cyclosporine and to achieve higher target sirolimus trough concentrations during concentration-controlled administration [ see Dosage and Administration (2.1), Drug Interactions (7.1)].

Lymphangioleiomyomatosis

In a clinical trial of patients with lymphangioleiomyomatosis, the median whole blood sirolimus trough concentration after 3 weeks of receiving sirolimus tablets at a dose of 2 mg/day was 6.8 ng/mL (interquartile range 4.6 to 9.0 ng/mL; n = 37).

Pharmacokinetics in Specific Populations

Hepatic Impairment

Sirolimus was administered as a single, oral dose to subjects with normal hepatic function and to patients with Child-Pugh classification A (mild), B (moderate), or C (severe) hepatic impairment. Compared with the values in the normal hepatic function group, the patients with mild, moderate, and severe hepatic impairment had 43%, 94%, and 189% higher mean values for sirolimus AUC, respectively, with no statistically significant differences in mean Cmax. As the severity of hepatic impairment increased, there were steady increases in mean sirolimus t1/2, and decreases in the mean sirolimus clearance normalized for body weight (CL/F/kg).

The maintenance dose of sirolimus should be reduced by approximately one third in patients with mild to moderate hepatic impairment and by approximately one half in patients with severe hepatic impairment [ see Dosage and Administration (2.5)]. It is not necessary to modify the sirolimus loading dose in patients with mild, moderate, and severe hepatic impairment. Therapeutic drug monitoring is necessary in all patients with hepatic impairment [ see Dosage and Administration (2.7)].

Renal Impairment

The effect of renal impairment on the pharmacokinetics of sirolimus is not known. However, there is minimal (2.2%) renal excretion of the drug or its metabolites in healthy volunteers. The loading and the maintenance doses of sirolimus need not be adjusted in patients with renal impairment [ see Dosage and Administration (2.6)].

Pediatric Renal Transplant Patients

Sirolimus pharmacokinetic data were collected in concentration-controlled trials of pediatric renal transplant patients who were also receiving cyclosporine and corticosteroids. The target ranges for trough concentrations were either 10–20 ng/mL for the 21 children receiving tablets, or 5–15 ng/mL for the one child receiving oral solution. The children aged 6–11 years (n = 8) received mean ± SD doses of 1.75 ± 0.71 mg/day (0.064 ± 0.018 mg/kg, 1.65 ± 0.43 mg/m^2). The children aged 12–18 years (n = 14) received mean ± SD doses of 2.79 ± 1.25 mg/day (0.053 ± 0.0150 mg/kg, 1.86 ± 0.61 mg/m^2). At the time of sirolimus blood sampling for pharmacokinetic evaluation, the majority (80%) of these pediatric patients received the sirolimus dose at 16 hours after the once-daily cyclosporine dose. See Table 6below.

TABLE 6: SIROLIMUS PHARMACOKINETIC PARAMETERS (MEAN ± SD) IN PEDIATRIC RENAL TRANSPLANT PATIENTS (MULTIPLE-DOSE CONCENTRATION CONTROL) [Sirolimus co-administered with cyclosporine oral solution [MODIFIED] (e.g., Neoral ® Oral Solution) and/or cyclosporine capsules [MODIFIED] (e.g., Neoral ® Soft Gelatin Capsules).] , [As measured by Liquid Chromatographic/Tandem Mass Spectrometric Method (LC/MS/MS)]
Age | n | Body weight | Cmax,ss | tmax,ss | Cmin,ss | AUCт,ss | CL/F [Oral-dose clearance adjusted by either body weight (kg) or body surface area (m 2).] | CL/F
(y) |  | (kg) | (ng/mL) | (h) | (ng/mL) | (ng∙h/mL) | (mL/h/kg) | (L/h/m^2)
6–11 | 8 | 27 ± 10 | 22.1 ± 8.9 | 5.88 ± 4.05 | 10.6 ± 4.3 | 356 ± 127 | 214 ± 129 | 5.4 ± 2.8
12–18 | 14 | 52 ± 15 | 34.5 ± 12.2 | 2.7 ± 1.5 | 14.7 ± 8.6 | 466 ± 236 | 136 ± 57 | 4.7 ± 1.9

Table 7 below summarizes pharmacokinetic data obtained in pediatric dialysis patients with chronically impaired renal function.

TABLE 7: SIROLIMUS PHARMACOKINETIC PARAMETERS (MEAN ± SD) IN PEDIATRIC PATIENTS WITH END-STAGE KIDNEY DISEASE MAINTAINED ON HEMODIALYSIS OR PERITONEAL DIALYSIS (1, 3, 9, 15 mg/m^2SINGLE DOSE) [All subjects received sirolimus oral solution.]
Age Group (y) | n | tmax(h) | t1/2(h) | CL/F/WT (mL/h/kg)
5–11 | 9 | 1.1 ± 0.5 | 71 ± 40 | 580 ± 450
12–18 | 11 | 0.79 ± 0.17 | 55 ± 18 | 450 ± 232

Geriatric

Clinical studies of sirolimus did not include a sufficient number of patients >65 years of age to determine whether they will respond differently than younger patients. After the administration of sirolimus oral solution or tablets, sirolimus trough concentration data in renal transplant patients >65 years of age were similar to those in the adult population 18 to 65 years of age.

Gender

Sirolimus clearance in males was 12% lower than that in females; male subjects had a significantly longer t1/2than did female subjects (72.3 hours versus 61.3 hours). Dose adjustments based on gender are not recommended.

Race

In the phase 3 trials for the prophylaxis of organ rejection following renal transplantation using sirolimus solution or tablets and cyclosporine oral solution [MODIFIED] (e.g., Neoral®Oral Solution) and/or cyclosporine capsules [MODIFIED] (e.g., Neoral®Soft Gelatin Capsules) [ see Clinical Studies (14)], there were no significant differences in mean trough sirolimus concentrations over time between Black (n = 190) and non-Black (n = 852) patients during the first 6 months after transplantation.

Drug-Drug Interactions

Sirolimus is known to be a substrate for both cytochrome CYP3A4 and P-gp. The pharmacokinetic interaction between sirolimus and concomitantly administered drugs is discussed below. Drug interaction studies have not been conducted with drugs other than those described below.

Cyclosporine:Cyclosporine is a substrate and inhibitor of CYP3A4 and P-gp. Sirolimus should be taken 4 hours after administration of cyclosporine oral solution (MODIFIED) and/or cyclosporine capsules (MODIFIED). Sirolimus concentrations may decrease when cyclosporine is discontinued, unless the sirolimus dose is increased [ see Dosage and Administration (2.2), Drug Interactions (7.1)].

In a single-dose drug-drug interaction study, 24 healthy volunteers were administered 10 mg sirolimus tablets either simultaneously or 4 hours after a 300-mg dose of Neoral®Soft Gelatin Capsules (cyclosporine capsules [MODIFIED]). For simultaneous administration, mean Cmaxand AUC were increased by 512% and 148%, respectively, relative to administration of sirolimus alone. However, when given 4 hours after cyclosporine administration, sirolimus Cmaxand AUC were both increased by only 33% compared with administration of sirolimus alone.

In a single dose drug-drug interaction study, 24 healthy volunteers were administered 10 mg sirolimus oral solution either simultaneously or 4 hours after a 300 mg dose of Neoral®Soft Gelatin Capsules (cyclosporine capsules [MODIFIED]). For simultaneous administration, the mean Cmaxand AUC of sirolimus, following simultaneous administration were increased by 116% and 230%, respectively, relative to administration of sirolimus alone. However, when given 4 hours after Neoral®Soft Gelatin Capsules (cyclosporine capsules [MODIFIED]) administration, sirolimus Cmaxand AUC were increased by only 37% and 80%, respectively, compared with administration of sirolimus alone.

In a single-dose cross-over drug-drug interaction study, 33 healthy volunteers received 5 mg sirolimus oral solution alone, 2 hours before, and 2 hours after a 300 mg dose of Neoral®Soft Gelatin Capsules (cyclosporine capsules [MODIFIED]). When given 2 hours before Neoral®Soft Gelatin Capsules (cyclosporine capsules [MODIFIED]) administration, sirolimus Cmaxand AUC were comparable to those with administration of sirolimus alone. However, when given 2 hours after, the mean Cmaxand AUC of sirolimus were increased by 126% and 141%, respectively, relative to administration of sirolimus alone.

Mean cyclosporine Cmaxand AUC were not significantly affected when sirolimus oral solution was given simultaneously or when administered 4 hours after Neoral®Soft Gelatin Capsules (cyclosporine capsules [MODIFIED]). However, after multiple-dose administration of sirolimus given 4 hours after Neoral®in renal post-transplant patients over 6 months, cyclosporine oral-dose clearance was reduced, and lower doses of Neoral®Soft Gelatin Capsules (cyclosporine capsules [MODIFIED]) were needed to maintain target cyclosporine concentration.

In a multiple-dose study in 150 psoriasis patients, sirolimus 0.5, 1.5, and 3 mg/m^2/day was administered simultaneously with Sandimmune®Oral Solution (cyclosporine Oral Solution) 1.25 mg/kg/day. The increase in average sirolimus trough concentrations ranged between 67% to 86% relative to when sirolimus was administered without cyclosporine. The intersubject variability (% CV) for sirolimus trough concentrations ranged from 39.7% to 68.7%. There was no significant effect of multiple-dose sirolimus on cyclosporine trough concentrations following Sandimmune®Oral Solution (cyclosporine oral solution) administration. However, the % CV was higher (range 85.9% – 165%) than those from previous studies.

Diltiazem:Diltiazem is a substrate and inhibitor of CYP3A4 and P-gp; sirolimus concentrations should be monitored and a dose adjustment may be necessary [ see Drug Interactions (7.4)]. The simultaneous oral administration of 10 mg of sirolimus oral solution and 120 mg of diltiazem to 18 healthy volunteers significantly affected the bioavailability of sirolimus. Sirolimus Cmax, tmax, and AUC were increased 1.4-, 1.3-, and 1.6-fold, respectively. Sirolimus did not affect the pharmacokinetics of either diltiazem or its metabolites desacetyldiltiazem and desmethyldiltiazem.

Erythromycin:Erythromycin is a substrate and inhibitor of CYP3A4 and P-gp; co-administration of sirolimus oral solution or tablets and erythromycin is not recommended [ see Warnings and Precautions (5.20), Drug Interactions (7.2)]. The simultaneous oral administration of 2 mg daily of sirolimus oral solution and 800 mg q 8h of erythromycin as erythromycin ethylsuccinate tablets at steady state to 24 healthy volunteers significantly affected the bioavailability of sirolimus and erythromycin. Sirolimus Cmaxand AUC were increased 4.4- and 4.2-fold respectively and tmaxwas increased by 0.4 hr. Erythromycin Cmaxand AUC were increased 1.6- and 1.7-fold, respectively, and tmaxwas increased by 0.3 hr.

Ketoconazole:Ketoconazole is a strong inhibitor of CYP3A4 and P-gp; co-administration of sirolimus oral solution or tablets and ketoconazole is not recommended [ see Warnings and Precautions (5.20), Drug Interactions (7.2)]. Multiple-dose ketoconazole administration significantly affected the rate and extent of absorption and sirolimus exposure after administration of sirolimus oral solution, as reflected by increases in sirolimus Cmax, tmax, and AUC of 4.3-fold, 38%, and 10.9-fold, respectively. However, the terminal t½of sirolimus was not changed. Single-dose sirolimus did not affect steady-state 12-hour plasma ketoconazole concentrations.

Rifampin:Rifampin is a strong inducer of CYP3A4 and P-gp; co-administration of sirolimus oral solution or tablets and rifampin is not recommended. In patients where rifampin is indicated, alternative therapeutic agents with less enzyme induction potential should be considered [ see Warnings and Precautions (5.20), Drug Interactions (7.2)]. Pretreatment of 14 healthy volunteers with multiple doses of rifampin, 600 mg daily for 14 days, followed by a single 20-mg dose of sirolimus oral solution, greatly decreased sirolimus AUC and Cmaxby about 82% and 71%, respectively.

Verapamil:Verapamil is a substrate and inhibitor of CYP3A4 and P-gp; sirolimus concentrations should be monitored and a dose adjustment may be necessary; [ see Drug Interactions (7.4)]. The simultaneous oral administration of 2 mg daily of sirolimus oral solution and 180 mg q 12h of verapamil at steady state to 25 healthy volunteers significantly affected the bioavailability of sirolimus and verapamil. Sirolimus Cmaxand AUC were increased 2.3- and 2.2-fold, respectively, without substantial change in tmax. The Cmaxand AUC of the pharmacologically active S(-) enantiomer of verapamil were both increased 1.5-fold and tmaxwas decreased by 1.2 hr.

Drugs Which May Be Co-administered Without Dose Adjustment

Clinically significant pharmacokinetic drug-drug interactions were not observed in studies of drugs listed below. Sirolimus and these drugs may be co-administered without dose adjustments.

- Acyclovir
- Atorvastatin
- Digoxin
- Glyburide
- Nifedipine
- Norgestrel/ethinyl estradiol (Lo/Ovral ®)
- Prednisolone
- Sulfamethoxazole/trimethoprim (Bactrim ®)

Other Drug-Drug Interactions

Co-administration of sirolimus with other known strong inhibitors of CYP3A4 and/or P-gp (such as voriconazole, itraconazole, telithromycin, or clarithromycin) or other known strong inducers of CYP3A4 and/or P-gp (such as rifabutin) is not recommended [ see Warnings and Precautions (5.20), Drug Interactions (7.2)]. In patients in whom strong inhibitors or inducers of CYP3A4 are indicated, alternative therapeutic agents with less potential for inhibition or induction of CYP3A4 should be considered.

Care should be exercised when drugs or other substances that are substrates and/or inhibitors or inducers of CYP3A4 are administered concomitantly with sirolimus. Other drugs that have the potential to increase sirolimus blood concentrations include (but are not limited to):

- Calcium channel blockers: nicardipine.
- Antifungal agents: clotrimazole, fluconazole.
- Antibiotics: troleandomycin.
- Gastrointestinal prokinetic agents: cisapride, metoclopramide.
- Other drugs: bromocriptine, cimetidine, danazol, letermovir, protease inhibitors (e.g., for HIV and hepatitis C that include drugs such as ritonavir, indinavir, boceprevir, and telaprevir).

Other drugs that have the potential to decrease sirolimus concentrations include (but are not limited to):

- Anticonvulsants: carbamazepine, phenobarbital, phenytoin.
- Antibiotics: rifapentine.

Other Drug-Food Interactions

Grapefruit juice reduces CYP3A4-mediated drug metabolism. Grapefruit juice must not be taken with sirolimus [ see Drug Interactions (7.3)].

Drug-Herb Interactions

St. John's Wort (Hypericum perforatum) induces CYP3A4 and P-gp. Since sirolimus is a substrate for both cytochrome CYP3A4 and P-gp, there is the potential that the use of St. John's Wort in patients receiving sirolimus could result in reduced sirolimus concentrations [ see Drug Interactions (7.4)].

13 NONCLINICAL TOXICOLOGY

13.1 Carcinogenesis, Mutagenesis, Impairment of Fertility

Carcinogenicity studies were conducted in mice and rats. In an 86-week female mouse study at sirolimus doses 30 to 120 times higher than the 2 mg daily clinical dose (adjusted for body surface area), there was a statistically significant increase in malignant lymphoma at all dose levels compared with controls. In a second mouse study at dosages that were approximately 3 to 16 times the clinical dose (adjusted for body surface area), hepatocellular adenoma and carcinoma in males were considered sirolimus-related. In the 104-week rat study at dosages equal to or lower than the clinical dose of 2 mg daily (adjusted for body surface area), there were no significant findings.

Sirolimus was not genotoxic in the in vitrobacterial reverse mutation assay, the Chinese hamster ovary cell chromosomal aberration assay, the mouse lymphoma cell forward mutation assay, or the in vivomouse micronucleus assay.

When female rats were treated by oral gavage with sirolimus and mated to untreated males, female fertility was decreased at 0.5 mg/kg (2.5-fold the clinical dose of 2 mg, on a body surface area basis) due to decreased implantation. In addition, reduced ovary and uterus weight were observed. The NOAEL for female rat fertility was 0.1 mg/kg (0.5-fold the clinical dose of 2 mg).

When male rats were treated by oral gavage with sirolimus and mated to untreated females, male fertility was decreased at 2 mg/kg (9.7-fold the clinical dose of 2 mg, on a body surface area basis). Atrophy of testes, epididymides, prostate, seminiferous tubules, and reduced sperm counts were observed. The NOAEL for male rat fertility was 0.5 mg/kg (2.5-fold the clinical dose of 2 mg).

Testicular tubular degeneration was also seen in a 4-week intravenous study of sirolimus in monkeys at 0.1 mg/kg (1-fold the clinical dose of 2 mg, on a body surface area basis).

14 CLINICAL STUDIES

14.1 Prophylaxis of Organ Rejection in Renal Transplant Patients

Sirolimus Oral Solution

The safety and efficacy of sirolimus oral solution for the prevention of organ rejection following renal transplantation were assessed in two randomized, double-blind, multicenter, controlled trials. These studies compared two dose levels of sirolimus oral solution (2 mg and 5 mg, once daily) with azathioprine (Study 1) or placebo (Study 2) when administered in combination with cyclosporine and corticosteroids. Study 1 was conducted in the United States at 38 sites. Seven hundred nineteen (719) patients were enrolled in this trial and randomized following transplantation; 284 were randomized to receive sirolimus oral solution 2 mg/day; 274 were randomized to receive sirolimus oral solution 5 mg/day, and 161 to receive azathioprine 2–3 mg/kg/day. Study 2 was conducted in Australia, Canada, Europe, and the United States, at a total of 34 sites. Five hundred seventy-six (576) patients were enrolled in this trial and randomized before transplantation; 227 were randomized to receive sirolimus oral solution 2 mg/day; 219 were randomized to receive sirolimus oral solution 5 mg/day, and 130 to receive placebo. In both studies, the use of antilymphocyte antibody induction therapy was prohibited. In both studies, the primary efficacy endpoint was the rate of efficacy failure in the first 6 months after transplantation. Efficacy failure was defined as the first occurrence of an acute rejection episode (confirmed by biopsy), graft loss, or death.

The tables below summarize the results of the primary efficacy analyses from these trials. Sirolimus oral solution, at doses of 2 mg/day and 5 mg/day, significantly reduced the incidence of efficacy failure (statistically significant at the <0.025 level; nominal significance level adjusted for multiple [2] dose comparisons) at 6 months following transplantation compared with both azathioprine and placebo.

TABLE 8: INCIDENCE (%) OF EFFICACY FAILURE AT 6 AND 24 MONTHS FOR STUDY 1 [Patients received cyclosporine and corticosteroids.] , [Includes patients who prematurely discontinued treatment.]
Parameter | Sirolimus Oral Solution 2 mg/day (n = 284) | Sirolimus Oral Solution 5 mg/day (n = 274) | Azathioprine 2–3 mg/kg/day (n = 161)
Efficacy failure at 6 months [Primary endpoint.] | 18.7 | 16.8 | 32.3
Components of efficacy failure
Biopsy-proven acute rejection | 16.5 | 11.3 | 29.2
Graft loss | 1.1 | 2.9 | 2.5
Death | 0.7 | 1.8 | 0
Lost to follow-up | 0.4 | 0.7 | 0.6
Efficacy failure at 24 months | 32.8 | 25.9 | 36.0
Components of efficacy failure
Biopsy-proven acute rejection | 23.6 | 17.5 | 32.3
Graft loss | 3.9 | 4.7 | 3.1
Death | 4.2 | 3.3 | 0
Lost to follow-up | 1.1 | 0.4 | 0.6

TABLE 9: INCIDENCE (%) OF EFFICACY FAILURE AT 6 AND 36 MONTHS FOR STUDY 2 [Patients received cyclosporine and corticosteroids.] , [Includes patients who prematurely discontinued treatment.]
Parameter | Sirolimus Oral Solution 2 mg/day (n = 227) | Sirolimus Oral Solution 5 mg/day (n = 219) | Placebo (n = 130)
Efficacy failure at 6 months [Primary endpoint.] | 30.0 | 25.6 | 47.7
Components of efficacy failure
Biopsy-proven acute rejection | 24.7 | 19.2 | 41.5
Graft loss | 3.1 | 3.7 | 3.9
Death | 2.2 | 2.7 | 2.3
Lost to follow-up | 0 | 0 | 0
Efficacy failure at 36 months | 44.1 | 41.6 | 54.6
Components of efficacy failure
Biopsy-proven acute rejection | 32.2 | 27.4 | 43.9
Graft loss | 6.2 | 7.3 | 4.6
Death | 5.7 | 5.9 | 5.4
Lost to follow-up | 0 | 0.9 | 0.8

Patient and graft survival at 1 year were co-primary endpoints. The following table shows graft and patient survival at 1 and 2 years in Study 1, and 1 and 3 years in Study 2. The graft and patient survival rates were similar in patients treated with sirolimus and comparator-treated patients.

TABLE 10: GRAFT AND PATIENT SURVIVAL (%) FOR STUDY 1 (12 AND 24 MONTHS) AND STUDY 2 (12 AND 36 MONTHS) [Patients received cyclosporine and corticosteroids.] , [Includes patients who prematurely discontinued treatment.]
Parameter | Sirolimus Oral Solution 2 mg/day | Sirolimus Oral Solution 5 mg/day | Azathioprine 2–3 mg/kg/day | Placebo
Study 1 | (n = 284) | (n = 274) | (n = 161)
Graft survival
Month 12 | 94.7 | 92.7 | 93.8
Month 24 | 85.2 | 89.1 | 90.1
Patient survival
Month 12 | 97.2 | 96.0 | 98.1
Month 24 | 92.6 | 94.9 | 96.3
Study 2 | (n = 227) | (n = 219) |  | (n = 130)
Graft survival
Month 12 | 89.9 | 90.9 |  | 87.7
Month 36 | 81.1 | 79.9 |  | 80.8
Patient survival
Month 12 | 96.5 | 95.0 |  | 94.6
Month 36 | 90.3 | 89.5 |  | 90.8

The reduction in the incidence of first biopsy-confirmed acute rejection episodes in patients treated with sirolimus compared with the control groups included a reduction in all grades of rejection.

In Study 1, which was prospectively stratified by race within center, efficacy failure was similar for sirolimus oral solution 2 mg/day and lower for sirolimus oral solution 5 mg/day compared with azathioprine in Black patients. In Study 2, which was not prospectively stratified by race, efficacy failure was similar for both sirolimus oral solution doses compared with placebo in Black patients. The decision to use the higher dose of sirolimus oral solution in Black patients must be weighed against the increased risk of dose-dependent adverse events that were observed with the sirolimus oral solution 5-mg dose [ see Adverse Reactions (6.1)].

TABLE 11: PERCENTAGE OF EFFICACY FAILURE BY RACE AT 6 MONTHS [Patients received cyclosporine and corticosteroids.] , [Includes patients who prematurely discontinued treatment.]
Parameter | Sirolimus Oral Solution 2 mg/day | Sirolimus Oral Solution 5 mg/day | Azathioprine 2–3 mg/kg/day | Placebo
Study 1
Black (n = 166) | 34.9 (n = 63) | 18.0 (n = 61) | 33.3 (n = 42)
Non-Black (n = 553) | 14.0 (n = 221) | 16.4 (n = 213) | 31.9 (n = 119)
Study 2
Black (n = 66) | 30.8 (n = 26) | 33.7 (n = 27) |  | 38.5 (n = 13)
Non-Black (n = 510) | 29.9 (n = 201) | 24.5 (n = 192) |  | 48.7 (n = 117)

Mean glomerular filtration rates (GFR) post-transplant were calculated by using the Nankivell equation at 12 and 24 months for Study 1, and 12 and 36 months for Study 2. Mean GFR was lower in patients treated with cyclosporine and sirolimus oral solution compared with those treated with cyclosporine and the respective azathioprine or placebo control.

TABLE 12: OVERALL CALCULATED GLOMERULAR FILTRATION RATES (Mean ± SEM, cc/min) BY NANKIVELL EQUATION POST-TRANSPLANT [Includes patients who prematurely discontinued treatment.] , [Patients who had a graft loss were included in the analysis with GFR set to 0.0.]
Parameter | Sirolimus Oral Solution 2 mg/day | Sirolimus Oral Solution 5 mg/day | Azathioprine 2–3 mg/kg/day | Placebo
Study 1
Month 12 | 57.4 ± 1.3 (n = 269) | 54.6 ± 1.3 (n = 248) | 64.1 ± 1.6) (n = 149)
Month 24 | 58.4 ± 1.5 (n = 221) | 52.6 ± 1.5 (n = 222) | 62.4 ± 1.9 (n = 132)
Study 2
Month 12 | 52.4 ± 1.5 (n = 211) | 51.5 ± 1.5 (n = 199) |  | 58.0 ± 2.1 (n = 117)
Month 36 | 48.1 ± 1.8 (n = 183) | 46.1 ± 2.0 (n = 177) |  | 53.4 ± 2.7 (n = 102)

Within each treatment group in Studies 1 and 2, mean GFR at one-year post-transplant was lower in patients who experienced at least one episode of biopsy-proven acute rejection, compared with those who did not.

Renal function should be monitored, and appropriate adjustment of the immunosuppressive regimen should be considered in patients with elevated or increasing serum creatinine levels [ see Warnings and Precautions (5.8)].

Sirolimus Tablets

The safety and efficacy of sirolimus oral solution and sirolimus tablets for the prevention of organ rejection following renal transplantation were demonstrated to be clinically equivalent in a randomized, multicenter, controlled trial [ see Clinical Pharmacology (12.3)].

14.2 Cyclosporine Withdrawal Study in Renal Transplant Patients

The safety and efficacy of sirolimus as a maintenance regimen were assessed following cyclosporine withdrawal at 3 to 4 months after renal transplantation. Study 3 was a randomized, multicenter, controlled trial conducted at 57 centers in Australia, Canada, and Europe. Five hundred twenty-five (525) patients were enrolled. All patients in this study received the tablet formulation. This study compared patients who were administered sirolimus, cyclosporine, and corticosteroids continuously with patients who received this same standardized therapy for the first 3 months after transplantation (pre-randomization period) followed by the withdrawal of cyclosporine. During cyclosporine withdrawal, the sirolimus dosages were adjusted to achieve targeted sirolimus whole blood trough concentration ranges (16 to 24 ng/mL until month 12, then 12 to 20 ng/mL thereafter, expressed as chromatographic assay values). At 3 months, 430 patients were equally randomized to either continue sirolimus with cyclosporine therapy or to receive sirolimus as a maintenance regimen following cyclosporine withdrawal.

Eligibility for randomization included no Banff Grade 3 acute rejection or vascular rejection episode in the 4 weeks before random assignment, serum creatinine ≤4.5 mg/dL, and adequate renal function to support cyclosporine withdrawal (in the opinion of the investigator). The primary efficacy endpoint was graft survival at 12 months after transplantation. Secondary efficacy endpoints were the rate of biopsy-confirmed acute rejection, patient survival, incidence of efficacy failure (defined as the first occurrence of either biopsy-proven acute rejection, graft loss, or death), and treatment failure (defined as the first occurrence of either discontinuation, acute rejection, graft loss, or death).

The following table summarizes the resulting graft and patient survival at 12, 24, and 36 months for this trial. At 12, 24, and 36 months, graft and patient survival were similar for both groups.

TABLE 13: GRAFT AND PATIENT SURVIVAL (%): STUDY 3 [Includes patients who prematurely discontinued treatment.]
Parameter | Sirolimus with Cyclosporine Therapy (n = 215) | Sirolimus Following Cyclosporine Withdrawal (n = 215)
Graft Survival
Month 12 [Primary efficacy endpoint.] | 95.3 [Survival including loss to follow-up as an event.] | 97.2
Month 24 | 91.6 | 94.0
Month 36 [Initial planned duration of the study.] | 87.0 | 91.6
Patient Survival
Month 12 | 97.2 | 98.1
Month 24 | 94.4 | 95.8
Month 36 | 91.6 | 94.0

The following table summarizes the results of first biopsy-proven acute rejection at 12 and 36 months. There was a significant difference in first biopsy-proven rejection rates between the two groups after randomization and through 12 months. Most of the post-randomization acute rejections occurred in the first 3 months following randomization.

TABLE 14: INCIDENCE OF FIRST BIOPSY-PROVEN ACUTE REJECTION (%) BY TREATMENT GROUP AT 36 MONTHS: STUDY 3 [Includes patients who prematurely discontinued treatment.] , [All patients received corticosteroids.]
Period | Sirolimus with Cyclosporine Therapy (n = 215) | Sirolimus Following Cyclosporine Withdrawal (n = 215)
Pre-randomization [Randomization occurred at 3 months ± 2 weeks.] | 9.3 | 10.2
Post-randomization through 12 months | 4.2 | 9.8
Post-randomization from 12 to 36 months | 1.4 | 0.5
Post-randomization through 36 months | 5.6 | 10.2
Total at 36 months | 14.9 | 20.5

Patients receiving renal allografts with ≥4 HLA mismatches experienced significantly higher rates of acute rejection following randomization to the cyclosporine withdrawal group, compared with patients who continued cyclosporine (15.3% versus 3.0%). Patients receiving renal allografts with ≤3 HLA mismatches demonstrated similar rates of acute rejection between treatment groups (6.8% versus 7.7%) following randomization.

The following table summarizes the mean calculated GFR in Study 3 (cyclosporine withdrawal study).

TABLE 15: CALCULATED GLOMERULAR FILTRATION RATES (mL/min) BY NANKIVELL EQUATION AT 12, 24, AND 36 MONTHS POST-TRANSPLANT: STUDY 3 [Includes patients who prematurely discontinued treatment.] , [Patients who had a graft loss were included in the analysis and had their GFR set to 0.0.] , [All patients received corticosteroids.]
Parameter | Sirolimus with Cyclosporine Therapy | Sirolimus Following Cyclosporine Withdrawal
Month 12
Mean ± SEM | 53.2 ± 1.5 (n = 208) | 59.3 ± 1.5 (n = 203)
Month 24
Mean ± SEM | 48.4 ± 1.7 (n = 203) | 58.4 ± 1.6 (n = 201)
Month 36
Mean ± SEM | 47.0 ± 1.8 (n = 196) | 58.5 ± 1.9 (n = 199)

The mean GFR at 12, 24, and 36 months, calculated by the Nankivell equation, was significantly higher for patients receiving sirolimus as a maintenance regimen following cyclosporine withdrawal than for those in the sirolimus with cyclosporine therapy group. Patients who had an acute rejection prior to randomization had a significantly higher GFR following cyclosporine withdrawal compared to those in the sirolimus with cyclosporine group. There was no significant difference in GFR between groups for patients who experienced acute rejection post-randomization.

Although the initial protocol was designed for 36 months, there was a subsequent amendment to extend this study. The results for the cyclosporine withdrawal group at months 48 and 60 were consistent with the results at month 36. Fifty-two percent (112/215) of the patients in the sirolimus with cyclosporine withdrawal group remained on therapy to month 60 and showed sustained GFR.

14.3 High-Immunologic Risk Renal Transplant Patients

Sirolimus was studied in a one-year, clinical trial in high risk patients (Study 4) who were defined as Black transplant recipients and/or repeat renal transplant recipients who lost a previous allograft for immunologic reasons and/or patients with high panel-reactive antibodies (PRA; peak PRA level >80%). Patients received concentration-controlled sirolimus and cyclosporine (MODIFIED), and corticosteroids per local practice. The sirolimus dose was adjusted to achieve target whole blood trough sirolimus concentrations of 10–15 ng/mL (chromatographic method) throughout the 12-month study period. The cyclosporine dose was adjusted to achieve target whole blood trough concentrations of 200–300 ng/mL through week 2, 150–200 ng/mL from week 2 to week 26, and 100–150 ng/mL from week 26 to week 52 [ see Clinical Pharmacology (12.3)] for the observed trough concentrations ranges. Antibody induction was allowed per protocol as prospectively defined at each transplant center, and was used in 88.4% of patients. The study was conducted at 35 centers in the United States. A total of 224 patients received a transplant and at least one dose of sirolimus and cyclosporine and was comprised of 77.2% Black patients, 24.1% repeat renal transplant recipients, and 13.5% patients with high PRA. Efficacy was assessed with the following endpoints, measured at 12 months: efficacy failure (defined as the first occurrence of biopsy-confirmed acute rejection, graft loss, or death), first occurrence of graft loss or death, and renal function as measured by the calculated GFR using the Nankivell formula. The table below summarizes the result of these endpoints.

TABLE 16: EFFICACY FAILURE, GRAFT LOSS OR DEATH AND CALCULATED GLOMERULAR FUNCTION RATES (mL/min) BY NANKIVELL EQUATION AT 12 MONTHS POST-TRANSPLANT: STUDY 4
Parameter | Sirolimus with Cyclosporine, Corticosteroids (n = 224)
Efficacy Failure (%) | 23.2
Graft Loss or Death (%) | 9.8
Renal Function (mean ± SEM) [Calculated glomerular filtration rate by Nankivell equation.] , [Patients who had graft loss were included in this analysis with GFR set to 0.] | 52.6 ± 1.6 (n = 222)

Patient survival at 12 months was 94.6%. The incidence of biopsy-confirmed acute rejection was 17.4% and the majority of the episodes of acute rejection were mild in severity.

14.4 Conversion from Calcineurin Inhibitors to Sirolimus in Maintenance Renal Transplant Patients

Conversion from calcineurin inhibitors (CNI) to sirolimus was assessed in maintenance renal transplant patients 6 months to 10 years post-transplant (Study 5). This study was a randomized, multicenter, controlled trial conducted at 111 centers globally, including US and Europe, and was intended to show that renal function was improved by conversion from CNI to sirolimus. Eight hundred thirty (830) patients were enrolled and stratified by baseline calculated glomerular filtration rate (GFR, 20–40 mL/min versus greater than 40 mL/min). In this trial there was no benefit associated with conversion with regard to improvement in renal function and a greater incidence of proteinuria in the sirolimus conversion arm. In addition, enrollment of patients with baseline calculated GFR less than 40 mL/min was discontinued due to a higher rate of serious adverse events, including pneumonia, acute rejection, graft loss and death [ see Adverse Reactions (6.4)].

This study compared renal transplant patients (6–120 months after transplantation) who were converted from calcineurin inhibitors to sirolimus, with patients who continued to receive calcineurin inhibitors. Concomitant immunosuppressive medications included mycophenolate mofetil (MMF), azathioprine (AZA), and corticosteroids. sirolimus was initiated with a single loading dose of 12–20 mg, after which dosing was adjusted to achieve a target sirolimus whole blood trough concentration of 8–20 ng/mL (chromatographic method). The efficacy endpoint was calculated GFR at 12 months post-randomization. Additional endpoints included biopsy-confirmed acute rejection, graft loss, and death. Findings in the patient stratum with baseline calculated GFR greater than 40 mL/min (sirolimus conversion, n = 497; CNI continuation, n = 246) are summarized below. There was no clinically or statistically significant improvement in Nankivell GFR compared to baseline.

TABLE 17: RENAL FUNCTION IN STABLE RENAL TRANSPLANT PATIENTS IN PATIENTS WITH BASELINE GFR >40 mL/min THE SIROLIMUS CONVERSION STUDY (STUDY 5)
Parameter | Sirolimus Conversion N=496 | CNI Continuation N=245 | Difference (95% CI)
GFR mL/min (Nankivell) at 1 year | 59.0 | 57.7 | 1.3 (-1.1, 3.7)
GFR mL/min (Nankivell) at 2 year | 53.7 | 52.1 | 1.6 (-1.4, 4.6)

The rates of acute rejection, graft loss, and death were similar at 1 and 2 years. Treatment-emergent adverse events occurred more frequently during the first 6 months after sirolimus conversion. The rates of pneumonia were significantly higher for the sirolimus conversion group.

While the mean and median values for urinary protein to creatinine ratio were similar between treatment groups at baseline, significantly higher mean and median levels of urinary protein excretion were seen in the sirolimus conversion arm at 1 year and at 2 years, as shown in the table below [ see Warnings and Precautions (5.9)]. In addition, when compared to patients who continued to receive calcineurin inhibitors, a higher percentage of patients had urinary protein to creatinine ratios >1 at 1 and 2 years after sirolimus conversion. This difference was seen in both patients who had a urinary protein to creatinine ratio ≤1 and those who had a protein to creatinine ratio >1 at baseline. More patients in the sirolimus conversion group developed nephrotic range proteinuria, as defined by a urinary protein to creatinine ratio >3.5 (46/482 [9.5%] versus 9/239 [3.8%]), even when the patients with baseline nephrotic range proteinuria were excluded. The rate of nephrotic range proteinuria was significantly higher in the sirolimus conversion group compared to the calcineurin inhibitor continuation group with baseline urinary protein to creatinine ratio >1 (13/29 versus 1/14), excluding patients with baseline nephrotic range proteinuria.

TABLE 18: MEAN AND MEDIAN VALUES FOR URINARY PROTEIN TO CREATININE RATIO (mg/mg) BETWEEN TREATMENT GROUPS AT BASELINE, 1 AND 2 YEARS IN THE STRATUM WITH BASELINE CALCULATED GFR >40 mL/min
Study period | Sirolimus Conversion |  |  | CNI Continuation
 | N | Mean ± SD | Median | N | Mean ± SD | Median | p-value
Baseline | 410 | 0.35 ± 0.76 | 0.13 | 207 | 0.28 ± 0.61 | 0.11 | 0.381
1 year | 423 | 0.88 ± 1.61 | 0.31 | 203 | 0.37 ± 0.88 | 0.14 | <0.001
2 years | 373 | 0.86 ± 1.48 | 0.32 | 190 | 0.47 ± 0.98 | 0.13 | <0.001

The above information should be taken into account when considering conversion from calcineurin inhibitors to sirolimus in stable renal transplant patients due to the lack of evidence showing that renal function improves following conversion, and the finding of a greater increment in urinary protein excretion, and an increased incidence of treatment-emergent nephrotic range proteinuria following conversion to sirolimus. This was particularly true among patients with existing abnormal urinary protein excretion prior to conversion.

In an open-label, randomized, comparative, multicenter study where kidney transplant patients were either converted from tacrolimus to sirolimus 3 to 5 months post-transplant (sirolimus group) or remained on tacrolimus, there was no significant difference in renal function at 2 years post-transplant. Overall, 44/131 (33.6%) discontinued treatment in the sirolimus group versus 12/123 (9.8%) in the tacrolimus group. More patients reported adverse events 130/131 (99.2%) versus 112/123 (91.1%) and more patients reported discontinuations from the treatment due to adverse events 28/131 (21.4%) versus 4/123 (3.3%) in the sirolimus group compared to the tacrolimus group.

The incidence of biopsy-confirmed acute rejection was higher for patients in the sirolimus group 11/131 (8.4%) compared to the tacrolimus group 2/123 (1.6%) through 2 years post-transplant. The rate of new-onset diabetes mellitus post-randomization, defined as 30 days or longer of continuous or at least 25 days non-stop (without gap) use of any diabetic treatment after randomization, a fasting glucose ≥126 mg/dL or a non-fasting glucose ≥200 mg/dL, was higher in the sirolimus group 15/82 (18.3%) compared to the tacrolimus group 4/72 (5.6%). A greater incidence of proteinuria, was seen in the sirolimus group 19/131 (14.5%) versus 2/123 (1.6%) in the tacrolimus group.

14.5 Conversion from a CNI-based Regimen to a Sirolimus-based Regimen in Liver Transplant Patients

Conversion from a CNI-based regimen to a sirolimus-based regimen was assessed in stable liver transplant patients 6–144 months post-transplant. The clinical study was a 2:1 randomized, multi-center, controlled trial conducted at 82 centers globally, including the US and Europe, and was intended to show that renal function was improved by conversion from a CNI to sirolimus without adversely impacting efficacy or safety. A total of 607 patients were enrolled.

The study failed to demonstrate superiority of conversion to a sirolimus-based regimen compared to continuation of a CNI-based regimen in baseline-adjusted GFR, as estimated by Cockcroft-Gault, at 12 months (62 mL/min in the sirolimus conversion group and 63 mL/min in the CNI continuation group). The study also failed to demonstrate non-inferiority, with respect to the composite endpoint consisting of graft loss and death (including patients with missing survival data) in the sirolimus conversion group compared to the CNI continuation group (6.6% versus 5.6%). The number of deaths in the sirolimus conversion group (15/393, 3.8%) was higher than in the CNI continuation group (3/214, 1.4%), although the difference was not statistically significant. The rates of premature study discontinuation (primarily due to adverse events or lack of efficacy), adverse events overall (infections, specifically), and biopsy-proven acute liver graft rejection at 12 months were all significantly greater in the sirolimus conversion group compared to the CNI continuation group.

14.6 Pediatric Renal Transplant Patients

Sirolimus was evaluated in a 36-month, open-label, randomized, controlled clinical trial at 14 North American centers in pediatric (aged 3 to <18 years) renal transplant patients considered to be at high-immunologic risk for developing chronic allograft nephropathy, defined as a history of one or more acute allograft rejection episodes and/or the presence of chronic allograft nephropathy on a renal biopsy. Seventy-eight (78) subjects were randomized in a 2:1 ratio to sirolimus (sirolimus target concentrations of 5 to 15 ng/mL, by chromatographic assay, n = 53) in combination with a calcineurin inhibitor and corticosteroids or to continue calcineurin-inhibitor-based immunosuppressive therapy (n = 25). The primary endpoint of the study was efficacy failure as defined by the first occurrence of biopsy-confirmed acute rejection, graft loss, or death, and the trial was designed to show superiority of sirolimus added to a calcineurin-inhibitor-based immunosuppressive regimen compared to a calcineurin-inhibitor-based regimen. The cumulative incidence of efficacy failure up to 36 months was 45.3% in the sirolimus group compared to 44.0% in the control group, and did not demonstrate superiority. There was one death in each group. The use of sirolimus in combination with calcineurin inhibitors and corticosteroids was associated with an increased risk of deterioration of renal function, serum lipid abnormalities (including, but not limited to, increased serum triglycerides and cholesterol), and urinary tract infections [ see Warnings and Precautions (5.8)]. This study does not support the addition of sirolimus to calcineurin-inhibitor-based immunosuppressive therapy in this subpopulation of pediatric renal transplant patients.

14.7 Lymphangioleiomyomatosis Patients

The safety and efficacy of sirolimus for treatment of lymphangioleiomyomatosis (LAM) were assessed in a randomized, double-blind, multicenter, controlled trial. This study compared sirolimus (dose-adjusted to maintain blood trough concentrations between 5–15 ng/mL) with placebo for a 12-month treatment period, followed by a 12-month observation period. Eighty-nine (89) patients were enrolled; 43 patients were randomized to receive placebo and 46 patients to receive sirolimus. The primary endpoint was the difference between the groups in the rate of change (slope) per month in forced expiratory volume in 1 second (FEV1). During the treatment period, the FEV1 slope was -12±2 mL per month in the placebo group and 1±2 mL per month in the sirolimus group (treatment difference = 13 mL (95% CI: 7, 18). The absolute between-group difference in the mean change in FEV1 during the 12-month treatment period was 153 mL, or approximately 11% of the mean FEV1 at enrollment. Similar improvements were seen for forced vital capacity (FVC). After discontinuation of sirolimus, the decline in lung function resumed in the sirolimus group and paralleled that in the placebo group (see Figure 1).

FIGURE 1: CHANGE IN FORCED EXPIRATORY VOLUME IN 1 SECOND (FEV1) DURING THE TREATMENT AND OBSERVATION PHASES OF THE STUDY IN LAM PATIENTS

The rate of change over 12 months of vascular endothelial growth factor-D (VEGF-D), a lymphangiogenic growth factor which has been shown to be elevated in patients with LAM, was significantly different in the sirolimus-treated group (-88.0 ± 16.6 pg/mL/month) compared to placebo (-2.42 ± 17.2 pg/mL/month) with a treatment difference of -86 pg/mL/month (95% CI: -133, -39). The absolute between-group difference in the mean change in VEGF-D during the 12-month treatment period was -1017.2, or approximately 50% of the mean VEGF-D at enrollment.

15 REFERENCES

Clinical Therapeutics, Volume 22, Supplement B, April 2000 [ see Dosage and Administration (2.5)].

16 HOW SUPPLIED/STORAGE AND HANDLING

Since sirolimus is not absorbed through the skin, there are no special precautions.

Do not use sirolimus after the expiration date. The expiration date refers to the last day of that month.

Sirolimus Tablets are available as follows:

0.5 mg, tan, triangular-shaped tablets marked "RAPAMUNE 0.5 mg" on one side;

NDC: 70518-4194-00

NDC: 70518-4194-01

PACKAGING: 100 in 1 BOX

PACKAGING: 1 in 1 POUCH

Sirolimus Tablets should be stored at 20°C to 25°C [USP Controlled Room Temperature] (68°F to 77°F). Dispense in a tight, light-resistant container as defined in the USP.

Repackaged and Distributed By:

Remedy Repack, Inc.

625 Kolter Dr. Suite #4 Indiana, PA 1-724-465-8762

17 PATIENT COUNSELING INFORMATION

Advise patients, their families, and their caregivers to read the Medication Guide and assist them in understanding its contents. The complete text of the Medication Guide is reprinted at the end of the document.

See FDA-Approved Medication Guide.

Repackaged By / Distributed By: RemedyRepack Inc.

625 Kolter Drive, Indiana, PA 15701

(724) 465-8762

17.1 Dosage

Patients should be given complete dosage instructions [ see FDA-Approved Medication Guide].

17.2 Skin Cancer Events

Advise patients that exposure to sunlight and ultraviolet (UV) light should be limited by wearing protective clothing and using a broad spectrum sunscreen with a high protection factor because of the increased risk for skin cancer [ see Warnings and Precautions (5.18)].

17.3 Pregnancy and Lactation

Advise female patients of reproductive potential to avoid becoming pregnant throughout treatment and for 12 weeks after sirolimus therapy has stopped. Sirolimus can cause fetal harm if taken during pregnancy. Advise a pregnant woman of the potential risk to her fetus. Before making a decision to breastfeed, inform the patient that the effects of breastfeeding in infants while taking this drug are unknown, but there is potential for serious adverse effects [ see Warnings and Precautions (5.15), Use in Specific Populations (8.1, 8.2, 8.3)].

17.4 Infertility

Inform male and female patients that sirolimus may impair fertility [ see Warnings and Precautions (5.16), Adverse Reactions (6.7), Use in Specific Populations (8.1, 8.3), Nonclinical Toxicology (13.1)].

MEDICATION GUIDE
Sirolimus Tablets

What is the most important information I should know about sirolimus?

Sirolimus can cause serious side effects, including:

1. Increased risk of getting infections.Serious infections can happen including infections caused by viruses, bacteria, and fungi (yeast). Your doctor may put you on medicine to help prevent some of these infections.

Call your doctor right away if you have symptoms of infection including fever or chills while taking sirolimus.

2. Increased risk of getting certain cancers.People who take sirolimus have a higher risk of getting lymphoma, and other cancers, especially skin cancer. Talk with your doctor about your risk for cancer.

Sirolimus has not been shown to be safe and effective in people who have had liver or lung transplants. Serious complications and death may happen in people who take sirolimus after a liver or lung transplant.You should not take sirolimusif you have had a liver or lung transplant without talking with your doctor.

See the section " What are the possible side effects of sirolimus?" for information about other side effects of sirolimus.

What is sirolimus?

Sirolimus is a prescription medicine used to prevent rejection (anti-rejection medicine) in people 13 years of age and older who have received a kidney transplant. Rejection is when your body's immune system recognizes the new organ as a "foreign" threat and attacks it.

Sirolimus is used with other medicines called cyclosporine (Gengraf, Neoral, Sandimmune), and corticosteroids. Your doctor will decide:

- if sirolimus is right for you, and
- how to best use it with cyclosporine and corticosteroids after your transplant.

It is not known if sirolimus is safe and effective in children under 13 years of age.

Sirolimus is a prescription medicine also used to treat lymphangioleiomyomatosis (LAM). LAM is a rare progressive lung disease that affects predominantly women of childbearing age.

Who should not take sirolimus?

Do not take sirolimus if you are allergic to sirolimus or any of the other ingredients in sirolimus. See the end of this leaflet for a complete list of ingredients in sirolimus.

What should I tell my doctor before taking sirolimus?

- have liver problems
- have skin cancer or it runs in your family
- have high cholesterol or triglycerides (fat in your blood)
- are pregnant or are a female who can become pregnant. Sirolimus can harm your unborn baby. You should not become pregnant during treatment with sirolimus and for 12 weeks after ending treatment with sirolimus. In order to avoid pregnancy, a female who can get pregnant should use effective birth control during treatment and for 12 weeks after your final dose of sirolimus. Talk with your doctor about what birth control method is right for you during this time. Tell your doctor right away if you become pregnant or think you are pregnant during treatment with sirolimus or within 12 weeks after your final dose of sirolimus.
- It is not known whether sirolimus passes into breast milk; however, there is a risk of serious side effects in breastfed infants. You and your doctor should decide about the best way to feed your baby if you take sirolimus.

Tell your doctor about all the medicines you take,including prescription and over-the-counter medicines, vitamins and herbal supplements. Using sirolimus with certain medicines may affect each other causing serious side effects.

Sirolimus may affect the way other medicines work, and other medicines may affect how sirolimus works.

Especially tell your doctor if you take:

- a medicine to lower your cholesterol or triglycerides
- cyclosporine (including Gengraf, Neoral, Sandimmune) or tacrolimus (Prograf) or other medicines that suppress the immune system
- an antibiotic
- an antifungal medicine
- a medicine for high blood pressure or heart problems
- an anti-seizure medicine
- medicines used to treat stomach acid, ulcers, or other gastrointestinal problems
- bromocriptine mesylate (Parlodel, Cycloset)
- danazol
- letermovir (Prevymis)
- medicines to treat HIV or hepatitis C
- St. John's Wort
- cannabidiol (Epidiolex)

How should I take sirolimus?

- Read the Instructions for Use that comes with your sirolimus for information about the right way to take sirolimus tablets.
- Take sirolimus exactly as your doctor tells you to take it.
- Your doctor will tell you how much sirolimus to take and when to take it. Do not change your dose of sirolimus unless your doctor tells you to.
- If you also take cyclosporine (Gengraf, Neoral, Sandimmune), you should take your sirolimus and cyclosporine about 4 hours apart.
- Do not stop taking sirolimus or your other anti-rejection medicines unless your doctor tells you to.
- Your doctor will check the levels of sirolimus in your blood. Your doctor may change your dose of sirolimus depending on your blood test results.
- Sirolimus is taken by mouth 1 time each day.
- Do not crush, chew, or split sirolimus tablets. Tell your doctor if you cannot swallow sirolimus tablets. Your doctor can prescribe sirolimus as a solution.
- Take each dose of sirolimus the same way, either with or without food. Food can affect the amount of medicine that gets into your bloodstream. Taking each dose of sirolimus the same way helps keep your blood levels of sirolimus more stable. Do not take sirolimus with grapefruit juice.
- If you have taken more medicine than you were told, contact a doctor or go to the nearest hospital emergency department right away.

What should I avoid while taking sirolimus?

- Avoid receiving live vaccines while taking sirolimus. Some vaccines may not work as well while you are taking sirolimus.
- Limit your time in sunlight and UV light. Cover your skin with clothing and use a broad spectrum sunscreen with a high protection factor because of the increased risk for skin cancer with sirolimus.

What are the possible side effects of sirolimus?

Sirolimus may cause serious side effects, including:

- See " What is the most important information I should know about sirolimus?"
- Serious allergic reactions. Tell your doctor or get medical help right awayif you get any of following symptoms of an allergic reaction:

- swelling of your face, eyes, or mouth
- trouble breathing or wheezing
- throat tightness

- chest pain or tightness
- feeling dizzy or faint
- rash or peeling of your skin

- Swelling (edema).Fluid may collect in your hands and feet and in various tissues of your body, including in the sac around your heart or lungs. Call your doctor if you have trouble breathing.
- Poor wound healing.Sirolimus may cause your wounds to heal slowly or not heal well. Tell your doctor if you have any redness or drainage, your wound does not heal, or the wound opens up.
- Increased levels of cholesterol and triglycerides (lipids or fat) in your blood.Your doctor should do blood tests to check your lipids during treatment with sirolimus. Your doctor may prescribe treatment with diet, exercise, or medicine if your lipid levels are too high. During treatment with sirolimus, your blood levels of cholesterol and triglycerides may remain high even if you follow your prescribed treatment plan.
- Effects on kidney function.When sirolimus is taken with cyclosporine (Gengraf, Neoral, Sandimmune), the function of your transplanted kidney may be affected. Your doctor should regularly do tests to check your kidney function while you are taking sirolimus with cyclosporine (Gengraf, Neoral, Sandimmune).
- Increased protein in your urine.Your doctor may regularly test your urine protein.
- Increased risk for viral infections.
  - Certain viruses can live in your body and cause active infections when your immune system is weak. BK virus can affect how your kidney works and cause your transplanted kidney to fail.
  - A certain virus can cause a rare serious brain infection called Progressive Multifocal Leukoencephalopathy (PML). PML usually causes death or severe disability. Call your doctor right away if you notice any new or worsening medical problems such as:
    - confusion
    - sudden change in thinking, walking, strength on one side of your body
    - other problems that have lasted over several days
- Lung or breathing problems.This can sometimes lead to death. Tell your doctor if you have a new or worsening cough, shortness of breath, difficulty breathing or any new breathing problems. Your doctor may need to stop sirolimus or lower your dose.
- Blood clotting problems.When sirolimus is taken with cyclosporine or tacrolimus, you may develop a blood clotting problem. Tell your doctor if you get any unexplained bleeding or bruising.
- Possible harm to your unborn baby.Sirolimus can harm your unborn baby. You should not become pregnant during treatment with sirolimus and for 12 weeks after ending treatment with sirolimus. See " What should I tell my doctor before taking sirolimus?".

The most common side effects of sirolimus in people with renal transplant include:

- high blood pressure
- pain (including stomach and joint pain)
- diarrhea
- headache
- fever

- urinary tract infection
- low red blood cell count (anemia)
- nausea
- low platelet count (cells that help blood to clot)
- high blood sugar (diabetes)

The most common side effects of sirolimus in people with LAM include:

- mouth sores
- diarrhea
- stomach pain
- nausea
- sore throat
- acne

- chest pain
- upper respiratory tract infection
- headache
- dizziness
- sore muscles

Other side effects that may occur with sirolimus:

- Sirolimus may affect fertility in females and may affect your ability to become pregnant. Talk to your healthcare provider if this is a concern for you.
- Sirolimus may affect fertility in males and may affect your ability to father a child. Talk to your healthcare provider if this is a concern for you.

Tell your doctor if you have any side effect that bothers you or that does not go away.

These are not all of the possible side effects of sirolimus. For more information ask your doctor or pharmacist.

Call your doctor for medical advice about side effects. You may report side effects to FDA at 1-800-FDA-1088.

How should I store sirolimus?

Sirolimus tablets:

- Store sirolimus tablets at room temperature between 68°F to 77°F (20°C to 25°C).
- Bottles: Keep the bottle of sirolimus tablets tightly closed.

Do not use sirolimus after the expiration date. The expiration date refers to the last day of that month.

Safely throw away medicine that is out of date or no longer needed.

Keep sirolimus and all medicines out of the reach of children.

General information about the safe and effective use of sirolimus.

Medicines are sometimes prescribed for purposes other than those listed in a Medication Guide. Do not use sirolimus for a condition for which it was not prescribed. Do not give sirolimus to other people even if they have the same symptoms that you have. It may harm them.

This Medication Guide summarizes the most important information about sirolimus. If you would like more information talk to your doctor. You can ask your pharmacist or doctor for information about sirolimus that is written for health professionals.

For more information about sirolimus call 1-877-446-3679.

What are the ingredients in sirolimus?

Active ingredients: sirolimus

Inactive ingredients: sirolimus tablets: sucrose, lactose, polyethylene glycol 8000, calcium sulfate, microcrystalline cellulose, pharmaceutical glaze, talc, titanium dioxide, magnesium stearate, povidone, poloxamer 188, polyethylene glycol 20,000, glyceryl monooleate, carnauba wax, dl-alpha tocopherol, and other ingredients. The 0.5 mg and 2 mg dosage strengths also contain yellow iron (ferric) oxide and brown iron (ferric) oxide.

For sirolimus oral tablets:

LAB-0621-8.0

This Medication Guide has been approved by the U.S. Food and Drug Administration. Revised Nov 2024

Repackaged By / Distributed By: RemedyRepack Inc.

625 Kolter Drive, Indiana, PA 15701

(724) 465-8762

PACKAGE LABEL

DRUG: Sirolimus

GENERIC: SIROLIMUS

DOSAGE: TABLET, SUGAR COATED

ADMINSTRATION: ORAL

NDC: 70518-4194-0

NDC: 70518-4194-1

COLOR: brown

SHAPE: TRIANGLE

SCORE: No score

SIZE: 8 mm

IMPRINT: RAPAMUNE;05;MG

PACKAGING: 1 in 1 POUCH

OUTER PACKAGING: 100 in 1 BOX

ACTIVE INGREDIENT(S):

- SIROLIMUS 0.5mg in 1

INACTIVE INGREDIENT(S):

- SUCROSE
- POLYETHYLENE GLYCOL 8000
- CALCIUM SULFATE, UNSPECIFIED FORM
- MICROCRYSTALLINE CELLULOSE
- TALC
- TITANIUM DIOXIDE
- MAGNESIUM STEARATE
- POVIDONE K30
- LACTOSE MONOHYDRATE
- POLOXAMER 188
- CARNAUBA WAX
- FERRIC OXIDE YELLOW
- .ALPHA.-TOCOPHEROL ACETATE
- GLYCERYL OLEATE